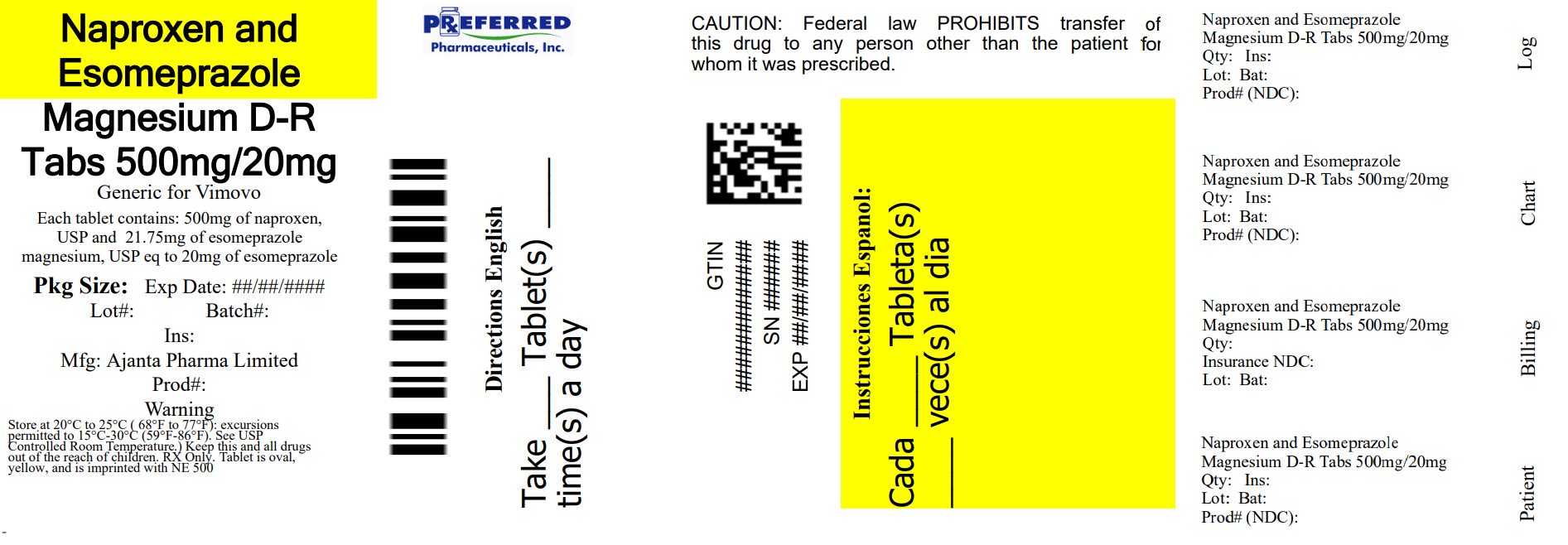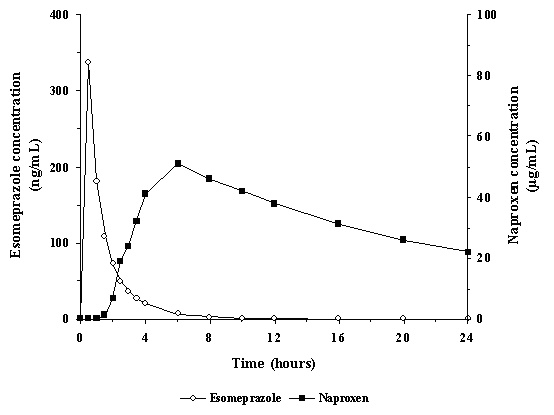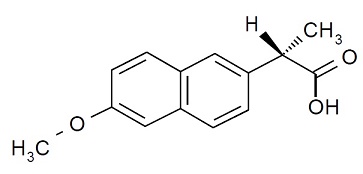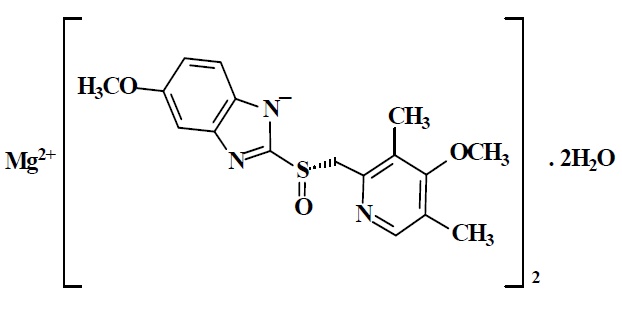 DRUG LABEL: Naproxen and esomeprazole magnesium
NDC: 68788-8766 | Form: TABLET, DELAYED RELEASE
Manufacturer: Preferred Pharmaceuticals Inc.
Category: prescription | Type: HUMAN PRESCRIPTION DRUG LABEL
Date: 20260120

ACTIVE INGREDIENTS: NAPROXEN 500 mg/1 1; ESOMEPRAZOLE MAGNESIUM TRIHYDRATE 20 mg/1 1
INACTIVE INGREDIENTS: MICROCRYSTALLINE CELLULOSE; CROSCARMELLOSE SODIUM; POVIDONE, UNSPECIFIED; SILICON DIOXIDE; MAGNESIUM STEARATE; METHACRYLIC ACID AND ETHYL ACRYLATE COPOLYMER; TALC; TRIETHYL CITRATE; HYPROMELLOSE, UNSPECIFIED; POLYETHYLENE GLYCOL, UNSPECIFIED; SODIUM LAURYL SULFATE; MAGNESIUM OXIDE; FERRIC OXIDE YELLOW; SHELLAC; FERROSOFERRIC OXIDE; PROPYLENE GLYCOL; AMMONIA

HIGHLIGHTS OF PRESCRIBING INFORMATION

These highlights do not include all the information needed to use NAPROXEN AND ESOMEPRAZOLE MAGNESIUM DELAYED-RELEASE TABLETS safely and effectively. See full prescribing information for NAPROXEN AND ESOMEPRAZOLE MAGNESIUM DELAYED-RELEASE TABLETS.
NAPROXEN and ESOMEPRAZOLE MAGNESIUM delayed-release tablets, for oral use
Initial U.S. Approval: 2010

RECENT MAJOR CHANGES

Warnings and Precautions, Serious skin Reactions (5.9) 07/2024

WARNING: RISK OF SERIOUS CARDIOVASCULAR AND GASTROINTESTINAL EVENTS

See full prescribing information for complete boxed warning.

- Nonsteroidal anti-inflammatory drugs (NSAIDs) cause an increased risk of serious cardiovascular thrombotic events, including myocardial infarction and stroke, which can be fatal. This risk may occur early in treatment and may increase with duration of use. (5.1)
- Naproxen and esomeprazole magnesium delayed-release tablets are contraindicated in the setting of coronary artery bypass graft (CABG) surgery. (4, 5.1)
- NSAIDs, including naproxen, a component of naproxen and esomeprazole magnesium delayed-release tablets, cause an increased risk of serious gastrointestinal (GI) adverse events including bleeding, ulceration, and perforation of the stomach or intestines, which can be fatal. These events can occur at any time during use and without warning symptoms. Elderly patients and patients with a prior history of peptic ulcer disease and/or GI bleeding are at greater risk for serious GI events. (5.2)

1 INDICATIONS AND USAGE

Naproxen and esomeprazole magnesium delayed-release tablet is a combination of naproxen, a non-steroidal anti-inflammatory drug (NSAID), and esomeprazole magnesium, a proton pump inhibitor (PPI) indicated in adult and adolescent patients 12 years of age and older weighing at least 38 kg, requiring naproxen for symptomatic relief of arthritis and esomeprazole magnesium to decrease the risk of developing naproxen-associated gastric ulcers.

The naproxen component of naproxen and esomeprazole magnesium delayed-release tablet is indicated for relief of signs and symptoms of:

- osteoarthritis, rheumatoid arthritis and ankylosing spondylitis in adults.
- juvenile idiopathic arthritis (JIA) in adolescent patients.

The esomeprazole magnesium component of naproxen and esomeprazole magnesium delayed-release tablet is indicated to decrease the risk of developing naproxen-associated gastric ulcers. (1)

Limitations of Use:

- Do not substitute naproxen and esomeprazole magnesium delayed-release tablets with the single-ingredient products of naproxen and esomeprazole magnesium. (1)
- Naproxen and esomeprazole magnesium delayed-release tablets are not recommended for initial treatment of acute pain because the absorption of naproxen is delayed compared to absorption from other naproxen-containing products. (1)
- Controlled studies do not extend beyond 6 months. (1)

2 DOSAGE AND ADMINISTRATION

Administration

- Use the lowest naproxen dose for the shortest duration consistent with individual patient treatment goals. (2.1, 5.1).
- If a total daily dose of less than 40 mg esomeprazole is more appropriate, a different treatment should be considered. (2.1)
- Swallow naproxen and esomeprazole magnesium delayed-release tablets whole with liquid at least 30 minutes before meals. (2.1)

Recommended Dosage (2.2)

Adolescents 12 years of age and older weighing 38 kg to less than 50 kg:

One naproxen and esomeprazole magnesium delayed-release tablet twice daily of 375 mg naproxen/20 mg of esomeprazole

Adults and adolescents 12 years of age and older greater than 50 kg:

One naproxen and esomeprazole magnesium delayed-release tablet twice daily of either:

- 375 mg naproxen/20 mg of esomeprazole; or
- 500 mg of naproxen/20 mg of esomeprazole

Renal or Hepatic Impairment (2.3)

- Avoid in moderate/severe renal impairment or severe hepatic impairment.
- Consider dose reduction in mild/moderate hepatic impairment.

3 DOSAGE FORMS AND STRENGTHS

Naproxen and esomeprazole magnesium delayed-release tablets (3):

- 375 mg enteric-coated naproxen /20 mg immediate-release esomeprazole
- 500 mg enteric-coated naproxen /20 mg immediate-release esomeprazole

4 CONTRAINDICATIONS

- Known hypersensitivity to naproxen, esomeprazole magnesium, substituted benzimidazoles, or to any components of the drug product including omeprazole. (4)
- History of asthma, urticaria, or other allergic-type reactions after taking aspirin or other NSAIDs. (4)
- In the setting of coronary artery bypass graft (CABG) surgery. (4)
- In patients receiving rilpivirine-containing products. (4, 7)

5 WARNINGS AND PRECAUTIONS

- Hepatotoxicity: Inform patients of warning signs and symptoms of hepatotoxicity. Discontinue if abnormal liver tests persist or worsen or if clinical signs and symptoms of liver disease develop. (5.3)
- Hypertension: Patients taking some antihypertensive medications may have impaired response to these therapies when taking NSAIDs. Monitor blood pressure. (5.4, 7)
- Heart Failure and Edema: Avoid use of naproxen and esomeprazole magnesium delayed-release tablets in patients with severe heart failure unless benefits are expected to outweigh risk of worsening heart failure. (5.5)
- Renal Toxicity: Monitor renal function in patients with renal or hepatic impairment, heart failure, dehydration, or hypovolemia. Avoid use of naproxen and esomeprazole magnesium delayed-release tablets in patients with advanced renal disease unless benefits are expected to outweigh risk of worsening renal function. (5.6)
- Anaphylactic Reactions: Seek emergency help if an anaphylactic reaction occurs. (5.7)
- Exacerbation of Asthma Related to Aspirin Sensitivity: Naproxen and esomeprazole magnesium delayed-release tablets are contraindicated in patients with aspirin-sensitive asthma. Monitor patients with preexisting asthma (without aspirin sensitivity). (5.8)
- Serious Skin Reactions: Discontinue naproxen and esomeprazole magnesium delayed-release tablets at first appearance of skin rash or other signs of hypersensitivity. (5.9)
- Drug Reaction with Eosinophilia and Systemic Symptoms (DRESS): Discontinue and evaluate clinically (5.10)
- Fetal Toxicity: Limit use of NSAIDs, including naproxen and esomeprazole magnesium delayed-release tablets, between about 20 weeks to 30 weeks in pregnancy due to the risk of oligohydramnios/fetal renal dysfunction. Avoid use of NSAIDs in women at about 30 weeks gestation and later in pregnancy due to the risks of oligohydramnios/fetal renal dysfunction and premature closure of the fetal ductus arteriosus (5.11, 8.1)
- Hematologic Toxicity: Monitor hemoglobin or hematocrit in patients with any signs of symptoms of anemia. (5.12, 7)
- Masking of Inflammation and Fever: Potential for diminished utility of diagnostic signs in detecting infections. (5.13)
- Laboratory Monitoring: Obtain CBC and chemistry profile periodically during treatment. Monitor hemoglobin periodically in patients on long-term treatment who have an initial value of 10 g or less. (5.14)
- Active Bleeding: Withdraw treatment in patients who experience active and clinically significant bleeding. (5.15)
- Concomitant NSAID Use: Do not use naproxen and esomeprazole magnesium delayed-release tablets with other naproxen-containing products or other non-aspirin NSAIDs. (5.16)
- Gastric Malignancy: In adults, symptomatic response to esomeprazole does not preclude the presence of gastric malignancy. Consider additional follow-up and diagnostic testing. (5.17)
- Acute Tubulointerstitial Nephritis: Discontinue treatment and evaluate patients. (5.18)
- Clostridium difficile-Associated Diarrhea: PPI therapy may be associated with increased risk of Clostridium difficile associated diarrhea. (5.19)
- Bone Fracture: Long-term and multiple daily dose PPI therapy may be associated with an increased risk for osteoporosis-related fractures of the hip, wrist or spine. (5.20)
- Cutaneous and Systemic Lupus Erythematosus: Mostly cutaneous, new onset or exacerbation of existing disease; discontinue naproxen and esomeprazole magnesium delayed-release tablets and refer to specialist for evaluation. (5.21)
- Interaction with Clopidogrel: Avoid concomitant use. (5.22, 7)
- Cyanocobalamin (Vitamin B-12) Deficiency: Daily long-term use (e.g., longer than 3 years) may lead to malabsorption or a deficiency of cyanocobalamin. (5.23)
- Hypomagnesemia and Mineral Metabolism: Reported rarely with prolonged treatment with PPIs. (5.24)
- Interaction with St. John’s Wort or Rifampin: Avoid concomitant use. (5.25, 7)
- Interactions with Diagnostic Investigations for Neuroendocrine Tumors: Increases in intragastric pH may result in hypergastrinemia, enterochromaffin-like cell hyperplasia, and increased Chromogranin A levels which may interfere with diagnostic investigations for neuroendocrine tumors. (5.26)
- Interaction with Methotrexate: Concomitant use with PPIs may elevate and/or prolong serum concentrations of methotrexate and/or its metabolite, possibly leading to toxicity. (5.27, 7)
- Fundic Gland Polyps: Risk increases with long-term PPI use, especially beyond one year. Use the shortest duration of therapy. (5.28)

6 ADVERSE REACTIONS

Most common adverse reactions in clinical trials (greater than 5%) are gastritis and diarrhea. (6.1)

To report SUSPECTED ADVERSE REACTIONS, contact Ajanta Pharma USA Inc. at 1-855-664-7744 or FDA at 1-800-FDA-1088 or www.fda.gov/medwatch.

7 DRUG INTERACTIONS

See full prescribing information for a list of clinically important drug interactions. (7)

8 USE IN SPECIFIC POPULATIONS

- Females and Males of Reproductive Potential: NSAIDs are associated with reversible infertility. Consider withdrawal of naproxen and esomeprazole magnesium delayed-release tablets in women who have difficulties conceiving. (8.3)

FULL PRESCRIBING INFORMATION

WARNING: RISK OF SERIOUS CARDIOVASCULAR AND GASTROINTESTINAL EVENTS

Cardiovascular Thrombotic Events

- Non-Steroidal Anti-inflammatory Drugs (NSAIDs), a component of naproxen and esomeprazole magnesium delayed-release tablets, cause an increased risk of serious cardiovascular thrombotic events, including myocardial infarction and stroke, which can be fatal. This risk may occur early in treatment and may increase with duration of use [see Warnings and Precautions (5.1)].
- Naproxen and esomeprazole magnesium delayed-release tablets are contraindicated in the setting of coronary artery bypass graft (CABG) surgery [see Contraindications (4), and Warnings and Precautions (5.1)].

Gastrointestinal Bleeding, Ulceration, and Perforation

- NSAIDs, a component of naproxen and esomeprazole magnesium delayed-release tablets cause an increased risk of serious gastrointestinal (GI) adverse events including bleeding, ulceration, and perforation of the stomach or intestines, which can be fatal. These events can occur at any time during use and without warning symptoms. Elderly patients and patients with a prior history of peptic ulcer disease and/or GI bleeding are at greater risk for serious GI events [see Warnings and Precautions (5.2)].

1 INDICATIONS AND USAGE

Naproxen and esomeprazole magnesium delayed-release tablets, a combination of naproxen and esomeprazole magnesium, is indicated in adult and adolescent patients 12 years of age and older weighing at least 38 kg, requiring naproxen for symptomatic relief of arthritis and esomeprazole magnesium to decrease the risk for developing naproxen-associated gastric ulcers.

The naproxen component of naproxen and esomeprazole magnesium delayed-release tablet is indicated for relief of signs and symptoms of:

- osteoarthritis, rheumatoid arthritis and ankylosing spondylitis in adults.
- juvenile idiopathic arthritis (JIA) in adolescent patients.

The esomeprazole magnesium component of naproxen and esomeprazole magnesium delayed-release tablet is indicated to decrease the risk of developing naproxen-associated gastric ulcers.

Limitations of Use:

- Do not substitute naproxen and esomeprazole magnesium delayed-release tablets with the single-ingredient products of naproxen and esomeprazole magnesium.
- Naproxen and esomeprazole magnesium delayed-release tablets are not recommended for initial treatment of acute pain because the absorption of naproxen is delayed compared to absorption from other naproxen-containing products.
- Controlled studies do not extend beyond 6 months [see Use in Specific Populations (8.4), Clinical Studies (14)].

2 DOSAGE AND ADMINISTRATION

2.1 Important Administration Instructions

- Use the lowest naproxen dose for the shortest duration consistent with individual patient treatment goals [see Warnings and Precautions (5.1)].
- Carefully consider the potential benefits and risks of naproxen and esomeprazole magnesium delayed-release tablets and other treatment options before deciding to use naproxen and esomeprazole magnesium delayed-release tablets.
- Naproxen and esomeprazole magnesium delayed-release tablets do not allow for administration of a lower daily dose of esomeprazole magnesium. If a total daily dose of less than 40 mg esomeprazole is more appropriate, a different treatment should be considered.
- Swallow naproxen and esomeprazole magnesium delayed-release tablets whole with liquid. Do not split, chew, crush or dissolve the tablet. Take naproxen and esomeprazole magnesium delayed-release tablets at least 30 minutes before meals.
- Patients should be instructed that if a dose is missed, it should be taken as soon as possible. However, if the next scheduled dose is due, the patient should not take the missed dose, and should be instructed to take the next dose on time. Patients should be instructed not to take 2 doses at one time to make up for a missed dose.
- Antacids may be used while taking naproxen and esomeprazole magnesium delayed-release tablets.

2.2 Recommended Dosage

The recommended dosage of naproxen and esomeprazole magnesium delayed-release tablets by indication is shown in the table:

Indication | Patient Population | Recommended Dosage
Rheumatoid Arthritis, Osteoarthritis, and Ankylosing Spondylitis | Adults | One naproxen and esomeprazole magnesium delayed-release tablet twice daily of either: 375 mg naproxen/20 mg of esomeprazole; or 500 mg naproxen/20 mg of esomeprazole
Juvenile Idiopathic Arthritis in Adolescent Patients 12 Years of Age and Older and Weighing at Least 38 kg | Greater than 50 kg | One naproxen and esomeprazole magnesium delayed-release tablet twice daily of either: 375 mg naproxen/20 mg of esomeprazole; or 500 mg naproxen/20 mg of esomeprazole
Juvenile Idiopathic Arthritis in Adolescent Patients 12 Years of Age and Older and Weighing at Least 38 kg | 38 kg to less than 50 kg | One naproxen and esomeprazole magnesium delayed-release tablet twice daily of: 375 mg naproxen/20 mg of esomeprazole

2.3 Use in Renal Impairment or Hepatic Impairment

Renal Impairment

Naproxen-containing products are not recommended for use in patients with moderate to severe or severe renal impairment (creatinine clearance less than 30 mL/min) [see Warnings and Precautions (5.6) , Use in Specific Populations (8.7)].

Hepatic Impairment

Monitor patients with mild to moderate hepatic impairment closely and consider a possible dose reduction based on the naproxen component of naproxen and esomeprazole magnesium delayed-release tablets.

Naproxen and esomeprazole magnesium delayed-release tablets should be avoided in patients with severe hepatic impairment [see Warnings and Precautions (5.3), Use in Specific Populations (8.6)].

3 DOSAGE FORMS AND STRENGTHS

Naproxen and esomeprazole magnesium delayed-release tablet is an oval, yellow, delayed-release tablets for oral administration containing either:

- 375 mg enteric-coated naproxen and 20 mg immediate-release esomeprazole tablets imprinted with NE 375 in black on one side and plain on other side, or
- 500 mg enteric-coated naproxen and 20 mg immediate-release esomeprazole tablets imprinted with NE 500 in black on one side and plain on other side.

4 CONTRAINDICATIONS

Naproxen and esomeprazole magnesium delayed-release tablet is contraindicated in the following patients:

- Known hypersensitivity (e.g., anaphylactic reactions and serious skin reactions) to naproxen, esomeprazole magnesium, substituted benzimidazoles, or to any components of the drug product, including omeprazole. Hypersensitivity reactions to esomeprazole may include anaphylaxis, anaphylactic shock, angioedema, bronchospasm, acute tubulointerstitial nephritis, and urticaria [see Warnings and Precautions (5.7, 5.8, 5.9, 5.18), Adverse Reaction (6.2)].
- History of asthma, urticaria, or allergic-type reactions after taking aspirin or other NSAIDs. Severe, sometimes fatal, anaphylactic reactions to NSAIDs have been reported in such patients [see Warnings and Precautions (5.7, 5.8)].
- In the setting of coronary artery bypass graft (CABG) surgery [see Warnings and Precautions (5.1)].
- Proton pump inhibitors (PPIs), including esomeprazole magnesium, are contraindicated in patients receiving rilpivirine-containing products [see Drug Interactions (7)].

5 WARNINGS AND PRECAUTIONS

5.1 Cardiovascular Thrombotic Events

Clinical trials of several COX-2 selective and nonselective NSAIDs of up to three years duration have shown an increased risk of serious cardiovascular (CV) thrombotic events, including myocardial infarction (MI), and stroke, which can be fatal. Based on available data, it is unclear that the risk for CV thrombotic events is similar for all NSAIDS. The relative increase in serious CV thrombotic events over baseline conferred by NSAID use appears to be similar in those with and without known CV disease or risk factors for CV disease. However, patients with known CV disease or risk factors had a higher absolute incidence of excess serious CV thrombotic events, due to their increased baseline rate. Some observational studies found that this increased risk of serious CV thrombotic events began as early as the first weeks of treatment. The increase in CV thrombotic risk has been observed most consistently at higher doses.

To minimize the potential risk for an adverse CV event in NSAID-treated patients, use the lowest effective dose for the shortest duration possible. Physicians and patients should remain alert for the development of such events, throughout the entire treatment course, even in the absence of previous CV symptoms. Patients should be informed about the symptoms of serious CV events and the steps to take if they occur.

There is no consistent evidence that concurrent use of aspirin mitigates the increased risk of serious CV thrombotic events associated with NSAID use. The concurrent use of aspirin and an NSAID, such as naproxen, increases the risk of serious gastrointestinal (GI) events [see Warnings and Precautions (5.2)].

Status Post Coronary Artery Bypass Graft (CABG) Surgery

Two large, controlled, clinical trials of a COX-2 selective NSAID for the treatment of pain in the first 10 days to 14 days following CABG surgery found an increased incidence of myocardial infarction and stroke. NSAIDs are contraindicated in the setting of CABG [see Contraindications (4)].

Post-MI Patients

Observational studies conducted in the Danish National Registry have demonstrated that patients treated with NSAIDs in the post-MI period were at increased risk of reinfarction, CV-related death, and all-cause mortality beginning in the first week of treatment. In this same cohort, the incidence of death in the first year post-MI was 20 per 100-person years in NSAID-treated patients compared to 12 per 100 person years in non-NSAID exposed patients. Although the absolute rate of death declined somewhat after the first year post-MI, the increased relative risk of death in NSAID users persisted over at least the next four years after follow-up.

Avoid the use of naproxen and esomeprazole magnesium delayed-release tablets in patients with a recent MI unless the benefits are expected to outweigh the risk of recurrent CV thrombotic events. If naproxen and esomeprazole magnesium delayed-release tablets are used in patients with a recent MI, monitor patients for signs of cardiac ischemia.

5.2 Gastrointestinal Bleeding, Ulceration, and Perforation

NSAIDs, including naproxen, can cause serious gastrointestinal (GI) adverse events including inflammation, bleeding, ulceration, and perforation of the esophagus, stomach, small intestine, or large intestine, which can be fatal. These serious adverse events can occur at any time, with or without warning symptoms, in patients treated with NSAIDs. Only one in five patients who develop a serious upper GI adverse event on NSAID therapy is symptomatic. Upper GI ulcers, gross bleeding, or perforation caused by NSAIDs occurred in approximately 1% of patients treated for 3 months to 6 months, and in about 2% to 4% of patients treated for one year. However, even short-term NSAID therapy is not without risk.

Risk Factors for GI Bleeding, Ulceration, and Perforation

Patients with a prior history of peptic ulcer disease and/or GI bleeding who used NSAIDs had a greater than 10-fold increased risk for developing a GI bleed compared to patients without these risk factors. Other factors that increase the risk for GI bleeding in patients treated with NSAIDs include longer duration of NSAID therapy; concomitant use of oral corticosteroids, aspirin, anticoagulants, or selective serotonin reuptake inhibitors (SSRIs); smoking; use of alcohol; older age; and poor general health status. Most postmarketing reports of fatal GI events are in elderly or debilitated patients. Additionally, patients with advanced liver disease and/or coagulopathy are at increased risk for GI bleeding.

Strategies to Minimize the GI Risks in NSAID-treated patients:

- Use the lowest effective dosage for the shortest possible duration.
- Avoid administration of more than one NSAID at a time.
- Avoid use in patients at higher risk unless benefits are expected to outweigh the increased risk of bleeding. For such as patients, as well as those with active GI bleeding, consider alternate therapies other than NSAIDs.
- Remain alert for signs and symptoms of GI ulceration and bleeding during NSAID therapy.
- If a serious GI adverse event is suspected, promptly initiate evaluation and treatment, and discontinue naproxen and esomeprazole magnesium delayed-release tablets until a serious GI adverse event is ruled out.
- In the setting of concomitant use of low-dose aspirin for cardiac prophylaxis, monitor patients more closely for evidence of GI bleeding [see Drug Interactions (7)].

NSAIDs should be given with care to patients with a history of inflammatory bowel disease (ulcerative colitis, Crohn’s disease) as their condition may be exacerbated.

5.3 Hepatotoxicity

Elevations of ALT or AST (three or more times the upper limit of the normal [ULN]) have been reported in approximately 1% of NSAID-treated patients in clinical trials. In addition, rare, and sometimes fatal, cases of severe hepatic injury, including jaundice and fatal fulminant hepatitis, liver necrosis, and hepatic failure have been reported.

Elevations of ALT or AST (less than three times ULN) may occur in up to 15% of patients treated with NSAIDs including naproxen.

Inform patients of the warning signs and symptoms of hepatotoxicity (e.g., nausea, fatigue, lethargy, diarrhea, pruritus, jaundice, right upper quadrant tenderness, and “flu-like” symptoms). If clinical signs and symptoms consistent with liver disease develop, or if systemic manifestations occur (e.g., eosinophilia, rash, etc.), discontinue naproxen and esomeprazole magnesium delayed-release tablets immediately, and perform a clinical evaluation of the patient.

Naproxen and esomeprazole magnesium delayed-release tablets should be avoided in patients with severe hepatic impairment [see Dosage and Administration (2), Use in Specific Populations (8.6), and Clinical Pharmacology (12.3)].

5.4 Hypertension

NSAIDs, including naproxen and esomeprazole magnesium delayed-release tablets, can lead to new onset of hypertension or worsening of preexisting hypertension, either of which may contribute to the increased incidence of CV events.

Patients taking angiotensin converting enzyme (ACE) inhibitors, thiazides diuretics, or loop diuretics may have impaired response to these therapies when taking NSAIDs [see Drug Interactions (7)].

Monitor blood pressure (BP) during the initiation of NSAID treatment and throughout the course of therapy.

5.5 Heart Failure and Edema

The Coxib and traditional NSAID Trialists’ Collaboration meta-analysis of randomized controlled trials demonstrated an approximately two-fold increase in hospitalizations for heart failure in COX-2 selective treated patients and nonselective NSAID-treated patients compared to placebo-treated patients. In a Danish National Registry study of patients with heart failure, NSAID use increased the risk of MI, hospitalization for heart failure, and death.

Additionally, fluid retention and edema have been observed in some patients treated with NSAIDs. Use of naproxen may blunt the CV effects of several therapeutic agents used to treat these medical conditions (e.g., diuretics, ACE inhibitors, or angiotensin receptor blockers [ARBs]) [see Drug Interactions (7)].

Avoid the use of naproxen and esomeprazole magnesium delayed-release tablets in patients with severe heart failure unless the benefits are expected to outweigh the risk of worsening heart failure. If naproxen and esomeprazole magnesium delayed-release tablets are used in patients with severe heart failure, monitor patients for signs and symptoms of worsening heart failure.

5.6 Renal Toxicity and Hyperkalemia

Renal Toxicity

Long-term administration of NSAIDs has resulted in renal papillary necrosis and other renal injury. Renal toxicity has also been seen in patients in whom renal prostaglandins have a compensatory role in the maintenance of renal perfusion. In these patients, administration of an NSAID may cause a dose-dependent reduction in prostaglandin formation and, secondarily, in renal blood flow, which may precipitate overt renal decompensation. Patients at greatest risk of this reaction are those with impaired renal function, dehydration, hypovolemia, heart failure, liver dysfunction, those taking diuretics and ACE-inhibitors or ARBs, and the elderly. Discontinuation of NSAID therapy was usually followed by recovery to the pretreatment state.

No information is available from controlled clinical studies regarding the use of naproxen and esomeprazole magnesium delayed-release tablets in patients with advanced renal disease. The renal effects of naproxen and esomeprazole magnesium delayed-release tablets may hasten the progression of renal dysfunction in patients with pre-existing renal disease.

Correct volume status in dehydrated or hypovolemic patients prior to initiating naproxen and esomeprazole magnesium delayed-release tablets. Monitor renal function in patients with renal or hepatic impairment, heart failure, dehydration, or hypovolemia during use of naproxen and esomeprazole magnesium delayed-release tablets [see Drug Interactions (7)]. Avoid the use of naproxen and esomeprazole magnesium delayed-release tablets in patients with advanced renal disease unless the benefits are expected to outweigh the risk of worsening renal failure. If naproxen and esomeprazole magnesium delayed-release tablets are used in patients with advanced renal disease, monitor patients for signs of worsening renal function.

Hyperkalemia

Increases in serum potassium concentration, including hyperkalemia, have been reported with use of NSAIDs, even in some patients without renal impairment. In patients with normal renal function, these effects have been attributed to a hyporeninemic-hypoaldosteronism state.

5.7 Anaphylactic Reactions

Naproxen has been associated with anaphylactic reactions in patients with and without known hypersensitivity to naproxen and in patients with aspirin-sensitive asthma [see Contraindications (4) and Warnings and Precautions (5.8)].

Seek emergency help if an anaphylactic reaction occurs.

5.8 Exacerbation of Asthma Related to Aspirin Sensitivity

A subpopulation of patients with asthma may have aspirin-sensitive asthma which may include chronic rhinosinusitis complicated by nasal polyps; severe, potentially fatal bronchospasm; and/or intolerance to aspirin and other NSAIDs. Because cross-reactivity between aspirin and other NSAIDs has been reported in such aspirin-sensitive patients, naproxen and esomeprazole magnesium delayed-release tablets are contraindicated in patients with this form of aspirin sensitivity [see Contraindications (4)]. When naproxen and esomeprazole magnesium delayed-release tablets are used in patients with preexisting asthma (without known aspirin sensitivity), monitor patients for changes in the signs and symptoms of asthma.

5.9 Serious Skin Reactions

NSAIDs, including naproxen, can cause serious skin adverse reactions such as exfoliative dermatitis, Stevens-Johnson Syndrome (SJS), and toxic epidermal necrolysis (TEN), which can be fatal. NSAIDs can also cause fixed drug eruption (FDE). FDE may present as a more severe variant known as generalized bullous fixed drug eruption (GBFDE), which can be life-threatening. PPIs can cause severe cutaneous adverse reactions, SJS, TEN, and acute generalized exanthematous pustulosis (AGEP) [see Adverse Reactions (6.2)].These serious events may occur without warning. Inform patients about the signs and symptoms of serious skin reactions, and to discontinue the use of naproxen and esomeprazole magnesium delayed-release tablets at the first appearance of skin rash or any other sign of hypersensitivity. Naproxen and esomeprazole magnesium delayed-release tablets are contraindicated in patients with previous serious skin reactions to NSAIDs [see Contraindications (4)].

5.10 Drug Reaction with Eosinophilia and Systemic Symptoms (DRESS)

Drug Reaction with Eosinophilia and Systemic Symptoms (DRESS) has been reported in patients taking NSAIDs and PPIs such as those contained in naproxen and esomeprazole magnesium delayed-release tablets. Some of these events have been fatal or life-threatening. DRESS typically, although not exclusively, presents with fever, rash, lymphadenopathy, and/or facial swelling. Other clinical manifestations may include hepatitis, nephritis, hematological abnormalities, myocarditis, or myositis. Sometimes symptoms of DRESS may resemble an acute viral infection. Eosinophilia is often present. Because this disorder is variable in its presentation, other organ systems not noted here may be involved. It is important to note that early manifestations of hypersensitivity, such as fever or lymphadenopathy, may be present even though rash is not evident. If such signs or symptoms are present, discontinue naproxen and esomeprazole magnesium delayed-release tablets and evaluate the patient immediately [see also Warnings and Precautions (5.9)].

5.11 Fetal Toxicity

Premature Closure of Fetal Ductus Arteriosus:
Avoid use of NSAIDs, including naproxen and esomeprazole magnesium delayed-release tablets, in pregnant women at about 30 weeks gestation and later. NSAIDs, including naproxen and esomeprazole magnesium delayed-release tablets, increase the risk of premature closure of the fetal ductus arteriosus at approximately this gestational age.

Oligohydramnios/Neonatal Renal Impairment:
Use of NSAIDs, including naproxen and esomeprazole magnesium delayed-release tablets, at about 20 weeks gestation or later in pregnancy may cause fetal renal dysfunction leading to oligohydramnios and, in some cases, neonatal renal impairment. These adverse outcomes are seen, on average, after days to weeks of treatment, although oligohydramnios has been infrequently reported as soon as 48 hours after NSAID initiation. Oligohydramnios is often, but not always, reversible with treatment discontinuation. Complications of prolonged oligohydramnios may, for example, include limb contractures and delayed lung maturation. In some postmarketing cases of impaired neonatal renal function, invasive procedures such as exchange transfusion or dialysis were required.

If NSAID treatment is necessary between about 20 weeks and 30 weeks gestation, limit naproxen and esomeprazole magnesium delayed-release tablets use to the lowest effective dose and shortest duration possible. Consider ultrasound monitoring of amniotic fluid if naproxen and esomeprazole magnesium delayed-release tablets treatment is needed in a pregnant woman. Discontinue naproxen and esomeprazole magnesium delayed-release tablets if oligohydramnios occurs and follow up according to clinical practice [see Use in Specific Populations (8.1)].

5.12 Hematologic Toxicity

Anemia has occurred in NSAID-treated patients. This may be due to occult or gross blood loss, fluid retention, or an incompletely described effect on erythropoiesis. If a patient treated with naproxen and esomeprazole magnesium delayed-release tablets have any signs or symptoms of anemia, monitor hemoglobin or hematocrit.

NSAIDs, including naproxen and esomeprazole magnesium delayed-release tablets, may increase the risk of bleeding events. Co-morbid conditions such as coagulation disorders or concomitant use of warfarin and other anticoagulants, antiplatelet agents (e.g., aspirin), and serotonin reuptake inhibitors (SSRIs) and serotonin norepinephrine reuptake inhibitors (SNRIs) may increase the risk. Monitor these patients for signs of bleeding [see Drug Interactions (7)].

5.13 Masking of Inflammation and Fever

The pharmacological activity of naproxen and esomeprazole magnesium delayed-release tablets in reducing inflammation, and possibly fever, may diminish the utility of diagnostic signs in detecting infections.

5.14 Laboratory Monitoring

Because serious GI bleeding, hepatotoxicity, and renal injury can occur without warning symptoms or signs, consider monitoring patients on long-term NSAID treatment with a CBC and chemistry profile periodically [see Warnings and Precautions (5.2, 5.3, 5.6)].

Patients with initial hemoglobin values of 10 g or less who are to receive long-term therapy should have hemoglobin values determined periodically.

5.15 Active Bleeding

When active and clinically significant bleeding from any source occurs in patients receiving naproxen and esomeprazole magnesium delayed-release tablets, the treatment should be withdrawn.

5.16 Concomitant NSAID Use

Naproxen and esomeprazole magnesium delayed-release tablets contain naproxen as one of its active ingredients. It should not be used with other naproxen-containing products since they all circulate in the plasma as the naproxen anion.

The concomitant use of naproxen and esomeprazole magnesium delayed-release tablets with any dose of a non-aspirin NSAID should be avoided due to the potential for increased risk of adverse reactions.

5.17 Presence of Gastric Malignancy

In adults, response to gastric symptoms with naproxen and esomeprazole magnesium delayed-release tablets do not preclude the presence of gastric malignancy. Consider additional gastrointestinal follow-up and diagnostic testing in adult patients who experience gastric symptoms during treatment with naproxen and esomeprazole magnesium delayed-release tablets or have a symptomatic relapse after completing treatment. In older patients, also consider an endoscopy.

5.18 Acute Tubulointerstitial Nephritis

Acute tubulointerstitial nephritis (TIN) has been observed in patients taking PPIs and may occur at any point during PPI therapy. Patients may present with varying signs and symptoms from symptomatic hypersensitivity reactions to non-specific symptoms of decreased renal function (e.g., malaise, nausea, anorexia). In reported case series, some patients were diagnosed on biopsy and in the absence of extra-renal manifestations (e.g., fever, rash or arthralgia).

Discontinue naproxen and esomeprazole magnesium delayed-release tablets and evaluate patients with suspected acute TIN [see Contraindications (4)].

5.19 Clostridium difficile-Associated Diarrhea

Published observational studies suggest that proton pump inhibitor (PPI) therapy like naproxen and esomeprazole magnesium delayed-release tablets may be associated with an increased risk of Clostridium difficile associated diarrhea, especially in hospitalized patients. This diagnosis should be considered for diarrhea that does not improve [see Adverse Reactions (6.2)].

Patients should use the lowest dose and shortest duration of PPI therapy appropriate to the condition being treated [see Dosage and Administration (2)].

5.20 Bone Fracture

Several published observational studies suggest that PPI therapy may be associated with an increased risk for osteoporosis-related fractures of the hip, wrist, or spine. The risk of fracture was increased in patients who received high-dose, defined as multiple daily doses, and long-term PPI therapy (a year or longer). Patients should use the lowest dose and shortest duration of PPI therapy appropriate to the condition being treated. Patients at risk for osteoporosis-related fractures should be managed according to the established treatment guidelines [see Dosage and Administration (2) , Adverse Reactions (6.2)].

Naproxen and esomeprazole magnesium delayed-release tablets (a combination PPI/NSAID) are approved for use twice a day and does not allow for administration of a lower daily dose of the PPI [see Dosage and Administration (2)].

5.21 Cutaneous and Systemic Lupus Erythematosus

Cutaneous lupus erythematosus (CLE) and systemic lupus erythematosus (SLE) have been reported in patients taking PPIs, including esomeprazole. These events have occurred as both new onset and an exacerbation of existing autoimmune disease. The majority of PPI-induced lupus erythematous cases were CLE.

The most common form of CLE reported in patients treated with PPIs was subacute CLE (SCLE) and occurred within weeks to years after continuous drug therapy inpatients ranging from infants to the elderly. Generally, histological findings were observed without organ involvement.

SLE is less commonly reported than CLE in patients receiving PPIs. PPI associated SLE is usually milder than non-drug induced SLE. Onset of SLE typically occurred within days to years after initiating treatment primarily in patients ranging from young adults to the elderly. The majority of patients presented with rash; however, arthralgia and cytopenia were also reported.

Avoid administration of PPIs for longer than medically indicated. If signs or symptoms consistent with CLE or SLE are noted in patients receiving naproxen and esomeprazole magnesium delayed-release tablets, discontinue drug and refer the patient to the appropriate specialist for evaluation. Most patients improve with discontinuation of the PPI alone in 4 to 12 weeks. Serological testing (e.g., ANA) may be positive and elevated serological test results may take longer to resolve than clinical manifestations.

5.22 Interaction with Clopidogrel

Avoid concomitant use of esomeprazole with clopidogrel. Clopidogrel is a prodrug. Inhibition of platelet aggregation by clopidogrel is entirely due to an active metabolite. The metabolism of clopidogrel to its active metabolite can be impaired by use with concomitant medications, such as esomeprazole, that inhibit CYP2C19 activity. Concomitant use of clopidogrel with 40 mg esomeprazole reduces the pharmacological activity of clopidogrel. When using esomeprazole, a component of naproxen and esomeprazole magnesium delayed-release tablets, consider alternative anti-platelet therapy [see Drug Interactions (7), Clinical Pharmacology (12.3)].

5.23 Cyanocobalamin (Vitamin B-12) Deficiency

Daily treatment with any acid-suppressing medications over a long period of time (e.g., longer than 3 years) may lead to malabsorption of cyanocobalamin (vitamin B-12) caused by hypo-or achlorhydria. Rare reports of cyanocobalamin deficiency occurring with acid-suppressing therapy have been reported in the literature. This diagnosis should be considered if clinical symptoms consistent with cyanocobalamin deficiency are observed.

5.24 Hypomagnesemia and Mineral Metabolism

Hypomagnesemia, symptomatic and asymptomatic, has been reported rarely in patients treated with PPIs for at least three months, in most cases after a year of therapy. Serious adverse events include tetany, arrhythmias, and seizures. Hypomagnesemia may lead to hypocalcemia and/or hypokalemia and may exacerbate underlying hypocalcemia in at-risk patients. In most patients, treatment of hypomagnesemia required magnesium replacement and discontinuation of the PPI.

For patients expected to be on prolonged treatment or who take PPIs with medications such as digoxin or drugs that may cause hypomagnesemia (e.g., diuretics), health care professionals may consider monitoring magnesium levels prior to initiation of PPI treatment and periodically [see Adverse Reactions (6.2)].

Consider monitoring magnesium and calcium levels prior to initiation of naproxen and esomeprazole magnesium delayed-release tablets and periodically while on treatment in patients with a preexisting risk of hypocalcemia (e.g., hypoparathyroidism). Supplement with magnesium and/or calcium, as necessary. If hypocalcemia is refractory to treatment, consider discontinuing the naproxen and esomeprazole magnesium delayed-release tablets.

5.25 Concomitant Use of St. John’s Wort or Rifampin with Naproxen and Esomeprazole Magnesium Delayed-Release Tablets

Drugs that induce CYP2C19 or CYP3A4 (such as St. John’s Wort or rifampin) can substantially decrease esomeprazole concentrations. Avoid concomitant use of naproxen and esomeprazole magnesium delayed-release tablets with St. John’s Wort or rifampin [see Drug Interactions (7)].

5.26 Interactions with Diagnostic Investigations for Neuroendocrine Tumors

Serum chromogranin A (CgA) levels increase secondary to drug-induced decreases in gastric acidity. The increased CgA level may cause false positive results in diagnostic investigations for neuroendocrine tumors. Providers should temporarily stop esomeprazole treatment at least 14 days before assessing CgA levels and consider repeating the test if initial CgA levels are high. If serial tests are performed (e.g. for monitoring), the same commercial laboratory should be used for testing, as reference ranges between tests may vary [see Drug Interactions (7), Clinical Pharmacology (12.2)].

5.27 Concomitant Use of Naproxen and Esomeprazole Magnesium Delayed-Release Tablets with Methotrexate

Literature suggests that concomitant use of PPIs with methotrexate (primarily at high dose; see methotrexate prescribing information) may elevate and prolong serum levels of methotrexate and/or its metabolite, possibly leading to methotrexate toxicities. In high-dose methotrexate administration a temporary withdrawal of the PPI may be considered in some patients [see Drug Interactions (7)].

5.28 Fundic Gland Polyps

PPI use is associated with an increased risk of fundic gland polyps that increases with long-term use, especially beyond one year. Most PPI users who developed fundic gland polyps were asymptomatic and fundic gland polyps were identified incidentally on endoscopy. Use the shortest duration of PPI therapy appropriate to the condition being treated.

6 ADVERSE REACTIONS

The following adverse reactions are discussed in greater detail in other sections of the labeling:

- Cardiovascular Thrombotic Events [see Warnings and Precautions (5.1)]
- GI Bleeding, Ulceration and Perforations [see Warnings and Precautions (5.2)]
- Hepatotoxicity [see Warnings and Precautions (5.3)]
- Hypertension [see Warnings and Precautions (5.4)]
- Heart Failure and Edema [see Warnings and Precautions (5.5)]
- Renal Toxicity and Hyperkalemia [see Warnings and Precautions (5.6)]
- Anaphylactic Reactions [see Warnings and Precautions (5.7)]
- Serious Skin Reactions [see Warnings and Precautions (5.9)]
- Drug Reaction with Eosinophilia and Systemic Symptoms (DRESS) [see Warnings and Precautions (5.10)]
- Fetal Toxicity [see Warnings and Precautions (5.11)]
- Hematologic Toxicity [see Warnings and Precautions (5.12)]
- Active Bleeding [see Warnings and Precautions (5.15)]
- Acute Tubulointerstitial Nephritis [see Warnings and Precautions (5.18)]
- Clostridium difficile-Associated Diarrhea [see Warnings and Precautions (5.19)]
- Bone Fracture [see Warnings and Precautions (5.20)]
- Cutaneous and Systemic Lupus Erythematosus [see Warnings and Precautions (5.21)]
- Cyanocobalamin (Vitamin B-12) Deficiency [see Warnings and Precautions (5.23)]
- Hypomagnesemia and Mineral Metabolism [see Warnings and Precautions (5.24)]
- Fundic Gland Polyps [see Warnings and Precautions (5.28)]

6.1 Clinical Trials Experience

Clinical Trials Experience with Naproxen and Esomeprazole Magnesium Delayed-Release Tablets

Because clinical trials are conducted under widely varying conditions, adverse reaction rates observed in the clinical trials of a drug cannot be directly compared to rates in the clinical trials of another drug and may not reflect the rates observed in practice.

The adverse reactions reported below are specific to the clinical trials with naproxen and esomeprazole magnesium delayed-release tablets.

The safety of naproxen and esomeprazole magnesium delayed-release tablets was evaluated in clinical studies involving 2,317 patients (aged 27 years to 90 years) and ranging from 3 months to 12 months. Patients received either 500 mg/20 mg of naproxen and esomeprazole magnesium delayed-release tablets twice daily (n=1,157), 500 mg of enteric-coated naproxen twice daily (n=426), or placebo (n=246). The average number of naproxen and esomeprazole magnesium delayed-release tablets doses taken over 12 months was 696+44.

The table below lists all adverse reactions, regardless of causality, occurring in greater than 2% of patients receiving naproxen and esomeprazole magnesium delayed-release tablets and higher in the naproxen and esomeprazole magnesium delayed-release tablets group than control from two clinical studies (Study 1 and Study 2). Both of these studies were randomized, multi-center, double-blind, parallel studies. The majority of patients were female (67%), white (86%). The majority of patients were 50 years to 69 years of age (83%). Approximately one quarter were on low-dose aspirin.

Table 1: Adverse Reactions* in Study 1 and Study 2 (endoscopic studies)
Preferred term | Naproxen and Esomeprazole Magnesium Delayed-Release Tablets 500 mg/20 mg twice daily (n=428) % | EC-Naproxen 500 mg twice daily (n=426) %
Gastritis | 17 | 14
Diarrhea | 6 | 5
Upper respiratory tract infection | 5 | 4
Flatulence | 4 | 3
Headache | 3 | 1
Urinary tract infection | 2 | 1
Dysgeusia | 2 | 1
*reported in greater than 2% of patients and higher in the naproxen and esomeprazole magnesium delayed-release tablets group than control

In Study 1 and Study 2, patients taking naproxen and esomeprazole magnesium delayed-release tablets had fewer premature discontinuations due to adverse reactions compared to patients taking enteric-coated naproxen alone (7.9% vs. 12.5% respectively). The most common reasons for discontinuations due to adverse events in the naproxen and esomeprazole magnesium delayed-release tablets treatment group were upper abdominal pain (1.2%, n=5), duodenal ulcer (0.7%, n=3) and erosive gastritis (0.7%, n=3). Among patients receiving enteric-coated naproxen, the most common reasons for discontinuations due to adverse events were duodenal ulcer 5.4% (n=23), dyspepsia 2.8% (n=12) and upper abdominal pain 1.2% (n=5). The proportion of patients discontinuing treatment due to any upper gastrointestinal adverse events (including duodenal ulcers) in patients treated with naproxen and esomeprazole magnesium delayed-release tablets was 4% compared to 12% for patients taking enteric-coated naproxen.

The table below lists all adverse reactions, regardless of causality, occurring in greater than 2% of patients and higher in the naproxen and esomeprazole magnesium delayed-release tablets group than placebo from 2 clinical studies conducted in patients with osteoarthritis of the knee (Study 3 and Study 4).

Table 2: Adverse Reactions* in Study 3 and Study 4
Preferred term | Naproxen and Esomeprazole Magnesium Delayed-Release Tablets 500 mg/20 mg twice daily (n=490) % | Placebo (n=246) %
Diarrhea | 6 | 4
Abdominal Pain Upper | 4 | 3
Constipation | 4 | 1
Dizziness | 3 | 2
Peripheral edema | 3 | 1
*reported in greater than 2% of patients and higher in the naproxen and esomeprazole magnesium delayed-release tablets group than placebo

The percentage of subjects who withdrew from the naproxen and esomeprazole magnesium delayed-release tablets treatment group in these studies due to treatment-emergent adverse events was 7%. There were no preferred terms in which more than 1% of subjects withdrew from any treatment group.

The long-term safety of naproxen and esomeprazole magnesium delayed-release tablets was evaluated in an open-label clinical trial of 239 patients, of which 135 patients received 500 mg/20 mg of naproxen and esomeprazole magnesium delayed-release tablets for 12 months. There were no differences in frequency or types of adverse reactions seen in the long-term safety study compared to shorter-term treatment in the randomized controlled studies.

Clinical Trials Experience with Naproxen and Other NSAIDs

In patients taking naproxen in clinical trials, the most frequent reported adverse experiences in approximately 1% to 10% of patients are:

Gastrointestinal: heartburn, nausea, dyspepsia, stomatitis

Central Nervous System: drowsiness, lightheadedness, vertigo

Dermatologic: pruritus, skin eruptions, ecchymoses, sweating, purpura

Special Senses: tinnitus, visual disturbances, hearing disturbances

Cardiovascular: palpitations

General: dyspnea, thirst

In patients taking NSAIDs, the following adverse experiences have also been reported in approximately 1% to 10% of patients.

Gastrointestinal: gross bleeding/perforation, GI ulcers (gastric/duodenal), vomiting

General: abnormal renal function, anemia, elevated liver enzymes, increased bleeding time, rashes

The following are additional adverse experiences reported in less than 1% of patients taking naproxen during clinical trials.

Gastrointestinal: pancreatitis

Hepatobiliary: jaundice

Hemic and Lymphatic: melena, thrombocytopenia, agranulocytosis

Nervous System: inability to concentrate

Dermatologic: skin rashes

In patients taking NSAIDs, the following adverse experiences have also been reported in less than 1% of patients.

Body as a Whole: fever, infection, sepsis, anaphylactic reactions, appetite changes, death

Cardiovascular: hypertension, tachycardia, syncope, arrhythmia, hypotension, myocardial infarction

Gastrointestinal: dry mouth, glossitis, eructation

Hepatobiliary: hepatitis, liver failure

Hemic and Lymphatic: rectal bleeding, lymphadenopathy, pancytopenia

Metabolic and Nutritional: weight changes

Nervous System: anxiety, asthenia, confusion, nervousness, paresthesia, somnolence, tremor, coma, hallucinations

Respiratory: asthma, respiratory depression, pneumonia

Dermatologic: exfoliative dermatitis

Special Senses: blurred vision, conjunctivitis

Urogenital: cystitis, dysuria, oliguria/polyuria, proteinuria

Clinical Trials Experience with Esomeprazole Magnesium

Additional adverse reactions that were reported as possibly or probably related to esomeprazole magnesium with an incidence of less than 1% are listed below by body system:

Body as a Whole: abdomen enlarged, allergic reaction, asthenia, back pain, chest pain, substernal chest pain, facial edema, hot flushes, fatigue, fever, flu-like disorder, generalized edema, malaise, pain, rigors

Cardiovascular: flushing, hypertension, tachycardia

Endocrine: goiter

Gastrointestinal: dyspepsia, dysphagia, dysplasia GI, epigastric pain, eructation, esophageal disorder, gastroenteritis, GI hemorrhage, GI symptoms not otherwise specified, hiccup, melena, mouth disorder, pharynx disorder, rectal disorder, serum gastrin increased, tongue disorder, tongue edema, ulcerative stomatitis, vomiting

Hearing: earache, tinnitus

Hematologic: anemia, anemia hypochromic, cervical lymphadenopathy, epistaxis, leukocytosis, leukopenia, thrombocytopenia

Hepatic: bilirubinemia, hepatic function abnormal, SGOT increased, SGPT increased

Metabolic/Nutritional: glycosuria, hyperuricemia, hyponatremia, increased alkaline phosphatase, thirst, vitamin B12 deficiency, weight increase, weight decrease

Musculoskeletal: arthralgia, arthritis aggravated, arthropathy, cramps, fibromyalgia syndrome, hernia, polymyalgia rheumatica

Nervous System/Psychiatric: anorexia, apathy, appetite increased, confusion, depression aggravated, hypertonia, nervousness, hypoesthesia, impotence, insomnia, migraine, migraine aggravated, paresthesia, sleep disorder, somnolence, tremor, vertigo, visual field defect

Reproductive: dysmenorrhea, menstrual disorder, vaginitis

Respiratory: asthma aggravated, coughing, dyspnea, larynx edema, pharyngitis, rhinitis, sinusitis

Skin and Appendages: acne, angioedema, dermatitis, pruritus, pruritus ani, rash, rash erythematous, rash maculo-papular, skin inflammation, sweating increased, urticaria

Special Senses: otitis media, parosmia, taste loss

Urogenital: abnormal urine, albuminuria, cystitis, dysuria, fungal infection, hematuria, micturition frequency, moniliasis, genital moniliasis, polyuria

Visual: conjunctivitis, vision abnormal

The following potentially clinically significant laboratory changes in clinical trials, irrespective of relationship to esomeprazole magnesium, were reported in less than or equal to 1% of patients: increased creatinine, uric acid, total bilirubin, alkaline phosphatase, ALT, AST, hemoglobin, white blood cell count, platelets, serum gastrin, potassium, sodium, thyroxine and thyroid stimulating hormone.

Decreases were seen in hemoglobin, white blood cell count, platelets, potassium, sodium, and thyroxine.

Endoscopic findings that were reported as adverse reactions include: duodenitis, esophagitis, esophageal stricture, esophageal ulceration, esophageal varices, gastric ulcer, hernia, benign polyps or nodules, Barrett’s esophagus, and mucosal discoloration.

6.2 Postmarketing Experience

The following adverse reactions have been identified during post-approval use of naproxen and esomeprazole magnesium delayed-release tablets. Because these reactions are reported voluntarily from a population of uncertain size, it is not always possible to reliably estimate their frequency or establish a causal relationship to drug exposure.

Naproxen and Esomeprazole Magnesium Delayed-Release Tablets

Body as a Whole: gait disturbance

Gastrointestinal: abdominal distension, abdominal pain, gastroesophageal reflux, hematochezia

Injury, Poisoning and Procedural Complications: contusion, fall

Musculoskeletal and Connective Tissue: joint swelling, muscle spasms

Urogenital: renal tubular necrosis

Naproxen

Body as a Whole: angioneurotic edema, menstrual disorders

Cardiovascular: congestive heart failure, vasculitis, pulmonary edema

Gastrointestinal: inflammation, bleeding (sometimes fatal, particularly in the elderly), ulceration, and obstruction of the upper or lower gastrointestinal tract, esophagitis, stomatitis, hematemesis, colitis, exacerbation of inflammatory bowel disease (ulcerative colitis, Crohn’s disease)

Hepatobiliary: hepatitis (some cases have been fatal)

Hemic and Lymphatic: eosinophilia, hemolytic anemia, aplastic anemia

Metabolic and Nutritional: hyperglycemia, hypoglycemia

Nervous System: depression, dream abnormalities, insomnia, malaise, myalgia, muscle weakness, aseptic meningitis, cognitive dysfunction, convulsions

Respiratory: eosinophilic pneumonitis

Dermatologic: alopecia, urticaria, toxic epidermal necrolysis, erythema multiforme, erythema nodosum, fixed drug eruption, lichen planus, pustular reaction, systemic lupus erythematoses, bullous reactions, including exfoliative dermatitis, Stevens-Johnson Syndrome (SJS), toxic epidermal necrolysis (TEN), fixed drug eruption (FDE), photosensitive dermatitis, photosensitivity reactions, including rare cases resembling porphyria cutanea tarda (pseudoporphyria) or epidermolysis bullosa. If skin fragility, blistering or other symptoms suggestive of pseudoporphyria occur, treatment should be discontinued and the patient monitored.

Special Senses: hearing impairment, corneal opacity, papillitis, retrobulbar optic neuritis, papilledema

Urogenital: glomerular nephritis, hematuria, hyperkalemia, interstitial nephritis, nephrotic syndrome, renal disease, renal failure, renal papillary necrosis, raised serum creatinine

Reproduction (female): infertility

Esomeprazole Magnesium

Blood and Lymphatic: agranulocytosis

Eye: blurred vision

Gastrointestinal: pancreatitis, microscopic colitis, fundic gland polyps

Hepatobiliary: hepatic failure, hepatitis with or without jaundice

Immune System: anaphylactic reaction/shock, systemic lupus erythematosus

Infections and Infestations: GI candidiasis, Clostridium difficile associated diarrhea

Metabolism and Nutritional Disorders: hypomagnesemia, hypocalcemia, hypokalemia [see Warnings and Precautions (5.24)],hyponatremia

Musculoskeletal and Connective Tissue: muscular weakness, myalgia, bone fracture

Nervous System: hepatic encephalopathy

Psychiatric: aggression, agitation, hallucination

Renal and Urinary: interstitial nephritis

Reproductive System and Breast:

gynecomastia, erectile dysfunction

Respiratory, Thoracic, and Mediastinal: bronchospasm

Skin and Subcutaneous Tissue: alopecia, erythema multiforme, photosensitivity, SJS, TEN (some fatal), DRESS, AGEP, cutaneous lupus erythematosus

7 DRUG INTERACTIONS

See Table 3 and Table 4 for clinically significant drug interactions and interactions with diagnostics with naproxen and esomeprazole magnesium.

Table 3: Clinically Significant Drug Interactions with Naproxen and Esomeprazole Magnesium – Affecting Drugs Co-Administered with Naproxen and Esomeprazole Magnesium Delayed-Release Tablets and Interactions with Diagnostics
Clinical Impact: | Naproxen; - Naproxen and anticoagulants such as warfarin have a synergistic effect on bleeding. The concomitant use of naproxen and anticoagulants have increased the risk of serious bleeding compared to the use of either drug alone. - Serotonin release by platelets plays an important role in hemostasis.; Case-control and cohort epidemiological studies showed that concomitant use of drugs that interfere with serotonin reuptake and an NSAID may potentiate the risk of bleeding more than an NSAID alone Esomeprazole Magnesium; - Increased INR and prothrombin time in patients treated with PPIs, including esomeprazole, and warfarin concomitantly. Increases in INR and prothrombin time may lead to abnormal bleeding and even death. - Concomitant use of esomeprazole 40 mg resulted in reduced plasma concentrations of the active metabolite of clopidogrel and a reduction in platelet inhibition [see Clinical Pharmacology (12.3)]. - There are no adequate combination studies of a lower dose of esomeprazole or a higher dose of clopidogrel in comparison with the approved dose of clopidogrel.
Intervention: | Monitor patients with concomitant use of naproxen and esomeprazole magnesium delayed-release tablets with anticoagulants (e.g., warfarin), antiplatelet agents (e.g., aspirin), selective serotonin reuptake inhibitors (SSRIs), and serotonin norepinephrine reuptake inhibitors (SNRIs) for signs of bleeding [see Warnings and Precautions (5.14)]. Clopidogrel: Avoid concomitant use of clopidogrel with naproxen and esomeprazole magnesium delayed-release tablets. Consider use of alternative anti-platelet therapy [see Warnings and Precautions (5.22)].
Aspirin
Clinical Impact: | A pharmacodynamics (PD) study has demonstrated an interaction in which lower dose naproxen (220mg/day or 220mg twice daily) interfered with the antiplatelet effect of low-dose immediate-release aspirin, with the interaction most marked during the washout period of naproxen [see Clinical Pharmacology (12.2.)]. There is reason to expect that the interaction would be present with prescription doses of naproxen or with enteric-coated low-dose aspirin; however, the peak interference with aspirin function may be later than observed in the PD study due to the longer washout period. Controlled clinical studies showed that the concomitant use of NSAIDs and analgesic doses of aspirin does not produce any greater therapeutic effect than the use of NSAIDs alone. In a clinical study, the concomitant use of an NSAID and aspirin was associated with a significantly increased incidence of GI adverse reactions as compared to use of the NSAID alone [see Warnings and Precautions (5.2)].
Intervention: | Because there may be an increased risk of cardiovascular events following discontinuation of naproxen due to the interference with the antiplatelet effect of aspirin during the washout period, for patients taking low-dose aspirin for cardioprotection who require intermittent analgesics, consider use of an NSAID that does not interfere with the antiplatelet effect of aspirin, or non-NSAID analgesics where appropriate. Concomitant use of naproxen and esomeprazole magnesium delayed-release tablets and analgesic doses of aspirin is not generally recommended because of the increased risk of bleeding [see Warnings and Precautions (5.12)]. Naproxen and esomeprazole magnesium delayed-release tablets are not a substitute for low dose aspirin for cardiovascular protection.
ACE Inhibitors, Angiotensin Receptor Blockers, and Beta-Blockers
Clinical Impact: | - NSAIDs may diminish the antihypertensive effect of angiotensin converting enzyme (ACE) inhibitors, angiotensin receptor blockers (ARBs), or beta-blockers (including propranolol). - In patients who are elderly, volume-depleted (including those on diuretic therapy), or have renal impairment, co-administration of an NSAID with ACE inhibitors or ARBs may result in deterioration of renal function, including possible acute renal failure. These effects are usually reversible.
Intervention: | - During concomitant use of naproxen and esomeprazole magnesium delayed-release tablets and ACE-inhibitors, ARBs, or beta-blockers, monitor blood pressure to ensure that the desired blood pressure is obtained. - During concomitant use of naproxen and esomeprazole magnesium delayed-release tablets and ACE-inhibitors or ARBs in patients who are elderly, volume-depleted or have impaired renal function, monitor for signs of worsening renal function [see Warnings and Precautions (5.6)].
Diuretics
Clinical Impact: | Clinical studies, as well as post-marketing observations, showed that NSAIDs reduced the natriuretic effect of loop diuretics (e.g., furosemide) and thiazide diuretics in some patients. This effect has been attributed to the NSAID inhibition of renal prostaglandin synthesis.
Intervention: | During concomitant use of naproxen and esomeprazole magnesium delayed-release tablets with diuretics, observe patients for signs of worsening renal function, in addition to assuring diuretic efficacy including antihypertensive effects [see Warnings and Precautions (5.6)].
Antiretrovirals
Clinical Impact: | The effect of esomeprazole magnesium on antiretroviral drugs is variable. The clinical importance and mechanisms behind these interactions are not always known.; - Decreased exposure of some antiretroviral drugs (e.g., rilpivirine, atazanavir, and nelfinavir) when used concomitantly with esomeprazole magnesium may reduce antiviral effect and promote the development of drug resistance [see Clinical Pharmacology (12.3)]. - Increased exposure of other antiretroviral drugs (e.g., saquinavir) when used concomitantly with esomeprazole magnesium may increase toxicity [see Clinical Pharmacology (12.3)]. - There are other antiretroviral drugs which do not result in clinically relevant interactions with esomeprazole magnesium.
Intervention: | Rilpivirine-containing products: Concomitant use with naproxen and esomeprazole magnesium delayed-release tablets are contraindicated [see Contraindications (4)]. Atazanavir: See prescribing information for atazanavir for dosing information. Nelfinavir: Avoid concomitant use with naproxen and esomeprazole magnesium delayed-release tablets. Saquinavir: See the prescribing information for saquinavir for monitoring of potential saquinavir-related toxicities. Other antiretrovirals: See prescribing information of specific drugs.
Cilostazol
Clinical Impact: | Increased exposure of cilostazol and one of its active metabolites (3,4-dihydro-cilostazol) when coadministered with omeprazole magnesium, the racemate of esomeprazole [see Clinical Pharmacology (12.3)].
Intervention: | Consider reducing the dose of cilostazol to 50 mg twice daily.
Digoxin
Clinical Impact: | Naproxen; - The concomitant use of naproxen with digoxin has been reported to increase the serum concentration and prolong the half-life of digoxin.; Esomeprazole Magnesium; - Potential for increased exposure of digoxin [see Clinical Pharmacology (12.3)].
Intervention: | Monitor digoxin concentrations during concomitant use of naproxen and esomeprazole magnesium delayed-release tablets. Dose adjustment of digoxin may be needed to maintain therapeutic drug concentrations.
Lithium
Clinical Impact: | NSAIDs have produced elevations of plasma lithium levels and reductions in renal lithium clearance. The mean minimum lithium concentration increased 15%, and the renal clearance decreased by approximately 20%. This effect has been attributed to NSAID inhibition of renal prostaglandin synthesis.
Intervention: | During concomitant use of naproxen and esomeprazole magnesium delayed-release tablets and lithium, monitor patients for signs of lithium toxicity.
Methotrexate
Clinical Impact: | Naproxen • Concomitant use of NSAIDs and methotrexate may increase the risk for methotrexate toxicity (e.g., neutropenia, thrombocytopenia, renal dysfunction). Esomeprazole Magnesium • Concomitant use of esomeprazole magnesium with methotrexate (primarily at high dose) may elevate and prolong serum concentrations of methotrexate and/or its metabolite hydroxymethotrexate, possibly leading to methotrexate toxicities [see Warnings and Precautions (5.27)].
Intervention: | During concomitant use of naproxen and esomeprazole magnesium delayed-release tablets and methotrexate, monitor patients for methotrexate toxicity. A temporary withdrawal of naproxen and esomeprazole magnesium delayed-release tablets may be considered in some patients receiving high-dose methotrexate.
Cyclosporine
Clinical Impact: | Concomitant use of naproxen and cyclosporine may increase cyclosporine’s nephrotoxicity.
Intervention: | During concomitant use of naproxen and esomeprazole magnesium delayed-release tablets and cyclosporine, monitor patients for signs of worsening renal function.
Tacrolimus
Clinical Impact: | Concomitant use of esomeprazole magnesium and tacrolimus may increase exposure of tacrolimus
Intervention: | During concomitant use of naproxen and esomeprazole magnesium delayed-release tablets and tacrolimus, monitor tacrolimus whole blood concentrations.
NSAIDs and Salicylates
Clinical Impact: | Concomitant use of naproxen with other NSAIDs or salicylates (e.g., diflunisal, salsalate) increases the risk of GI toxicity, with little or no increase in efficacy [see Warnings and Precautions (5.2)].
Intervention: | The concomitant use of naproxen and esomeprazole magnesium delayed-release tablets with other NSAIDs or salicylates is not recommended.
Pemetrexed
Clinical Impact: | Concomitant use of naproxen and esomeprazole magnesium delayed-release tablets and pemetrexed may increase the risk of pemetrexed-associated myelosuppression, renal, and GI toxicity (see the pemetrexed prescribing information).
Intervention: | During concomitant use of naproxen and esomeprazole magnesium delayed-release tablets and pemetrexed, in patients with renal impairment whose creatinine clearance ranges from 45 mL/min to 79 mL/min, monitor for myelosuppression, renal and GI toxicity.
Drugs Dependent on Gastric pH for Absorption (e.g., iron salts, erlotinib, mycophenoloate mofetil, ketoconazole)
Clinical Impact: | Esomeprazole magnesium can reduce the absorption of other drugs due to its effect on reducing intragastric acidity
Intervention: | Mycophenolate mofetil (MMF): Co-administration of omeprazole, of which esomeprazole magnesium is an enantiomer, in healthy subjects and in transplant patients receiving MMF has been reported to reduce the exposure to the active metabolite, mycophenolic acid (MPA), possibly due to a decrease in MMF solubility at an increased gastric pH. The clinical relevance of reduced MPA exposure on organ rejection has not been established in transplant patients receiving esomeprazole and MMF. Use naproxen and esomeprazole magnesium delayed-release tablets with caution in transplant patients receiving MMF [see Clinical Pharmacology (12.3)]. See the prescribing information for other drugs dependent on gastric pH for absorption.
Interactions with Investigations of Neuroendocrine Tumors
Clinical Impact: | Serum chromogranin A (CgA) levels increase secondary to PPI-induced decreases in gastric acidity. The increased CgA levels may cause false positive results in diagnostic investigations for neuroendocrine tumors [see Warnings and Precautions (5.26), Clinical Pharmacology (12.2)].
Intervention: | Temporarily stop naproxen and esomeprazole magnesium delayed-release tablets treatment at least 14 days before assessing CgA levels and consider repeating the test if initial CgA levels are high. If serial tests are performed (e.g. for monitoring), the same commercial laboratory should be used for testing, as reference ranges between tests may vary.
Diazepam
Clinical Impact: | Increased exposure of diazepam [see Clinical Pharmacology (12.3)].
Intervention: | Monitor patients for increased sedation and adjust the dose of diazepam as needed.

Table 4: Clinically Significant Interactions with Esomeprazole Magnesium --Affecting Co-Administered Drugs
CYP2C19 or CYP3A4 Inducers
Clinical Impact: | Decreased exposure of esomeprazole when used concomitantly with strong inducers [see Clinical Pharmacology (12.3)].
Intervention: | St. John’s Wort, rifampin: Avoid concomitant use with naproxen and esomeprazole magnesium delayed-release tablets [see Warnings and Precautions (5.25)].
CYP2C19 or CYP3A4 Inhibitors
Clinical Impact: | Increased exposure of esomeprazole [see Clinical Pharmacology (12.3)].
Intervention: | Voriconazole: Avoid concomitant use with naproxen and esomeprazole magnesium delayed-release tablets.

8 USE IN SPECIFIC POPULATIONS

8.1 Pregnancy

Risk Summary

Use of NSAIDs, including naproxen and esomeprazole magnesium delayed-release tablets, can cause premature closure of the fetal ductus arteriosus and fetal and renal dysfunction leading to oligohydramnios and, in some cases, neonatal renal impairment. Because of these risks, limit dose and duration of naproxen and esomeprazole magnesium delayed-release tablets use between about 20 weeks and 30 weeks of gestation and avoid naproxen and esomeprazole magnesium delayed-release tablets use at about 30 weeks of gestation and later in pregnancy (see Clinical Considerations, Data).

Premature Closure of the Fetal Ductus Arteriosus
Use of NSAIDs, including naproxen and esomeprazole magnesium delayed-release tablets, at about 30 weeks gestation or later in pregnancy increases the risk of premature closure of the fetal ductus arteriosus

Oligohydramnios/Neonatal Renal Impairment

Use of NSAIDs at about 20 weeks gestation or later in pregnancy has been associated with cases of fetal renal dysfunction leading to oligohydramnios, and in some cases, neonatal renal impairment.

Naproxen and esomeprazole magnesium delayed-release tablets contain naproxen and esomeprazole magnesium. Esomeprazole is the S-isomer of omeprazole.

Naproxen

Data from observational studies regarding potential embryofetal risks of NSAID use in women in the first or second trimesters of pregnancy are inconclusive. In animal reproduction studies, naproxen administered during organogenesis to rats and rabbits at doses less than the maximum recommended human daily dose of 1500 mg/day showed no evidence of harm to the fetus (see Data). Based on animal data, prostaglandins have been shown to have an important role in endometrial vascular permeability, blastocyst implantation, and decidualization. In animal studies, administration of prostaglandin synthesis inhibitors such as naproxen resulted in increased pre-and post-implantation loss.

Prostaglandins also have been shown to have an important role in fetal kidney development. In published animal studies, prostaglandin synthesis inhibitors have been reported to impair kidney development when administered at clinically relevant doses.

Esomeprazole

There are no human data for esomeprazole. However, available epidemiologic data for omeprazole (esomeprazole is the S-isomer of omeprazole) fail to demonstrate an increased risk of major congenital malformations or other adverse pregnancy outcomes with first trimester omeprazole use (see Data). In animal studies with administration of oral esomeprazole magnesium in rats, changes in bone morphology were observed in offspring of rats dosed through most of pregnancy and lactation at doses equal to or greater than approximately 34 times an oral human dose of 40 mg esomeprazole or 40 mg omeprazole. When maternal administration was confined to gestation only, there were no effects on bone physeal morphology in the offspring at any age [see Data].

The estimated background risks of major birth defects and miscarriage for the indicated population are unknown. All pregnancies have a background risk of birth defect, loss, or other adverse outcomes. In the U.S. general population, the estimated background risk of major birth defects and miscarriage in clinically recognized pregnancies is 2% to 4% and 15% to 20%, respectively.

Clinical Considerations
Fetal/Neonatal Adverse Reactions
Premature Closure of Fetal Ductus Arteriosus:
Avoid use of NSAIDs in women at about 30 weeks gestation and later in pregnancy, because NSAIDs, including naproxen and esomeprazole magnesium delayed-release tablets, can cause premature closure of the fetal ductus arteriosus (see Data).

Oligohydramnios/Neonatal Renal Impairment
If an NSAID is necessary at about 20 weeks gestation or later in pregnancy, limit the use to the lowest effective dose and shortest duration possible. If naproxen and esomeprazole magnesium delayed-release tablets treatment is needed in pregnant women, consider monitoring with ultrasound for oligohydramnios. If oligohydramnios occurs, discontinue naproxen and esomeprazole magnesium delayed-release tablets and follow up according to clinical practice (see Data).

Labor or Delivery

There are no studies on the effects of naproxen and esomeprazole magnesium delayed-release tablets during labor or delivery. In animal studies, NSAIDs, including naproxen, inhibit prostaglandin synthesis, cause delayed parturition, and increase the incidence of stillbirth.

Data

Human Data

Naproxen

When used to delay preterm labor, inhibitors of prostaglandin synthesis, including NSAIDs such naproxen, may increase the risk of neonatal complications such as necrotizing enterocolitis, patent ductus arteriosus and intracranial hemorrhage. Naproxen treatment given in late pregnancy to delay parturition has been associated with persistent pulmonary hypertension, renal dysfunction and abnormal prostaglandin E levels in preterm infants.

Premature Closure of Fetal Ductus Arteriosus:
Published literature reports that the use of NSAIDs at about 30 weeks of gestation and later in pregnancy may cause premature closure of the fetal ductus arteriosus.

Oligohydramnios/Neonatal Renal Impairment:
Published studies and postmarketing reports describe maternal NSAID use at about 20 weeks gestation or later in pregnancy associated with fetal renal dysfunction leading to oligohydramnios, and in some cases, neonatal renal impairment. These adverse outcomes are seen, on average, after days to weeks of treatment, although oligohydramnios has been infrequently reported as soon as 48 hours after NSAID initiation. In many cases, but not all, the decrease in amniotic fluid was transient and reversible with cessation of the drug. There have been a limited number of case reports of maternal NSAID use and neonatal renal dysfunction without oligohydramnios, some of which were irreversible. Some cases of neonatal renal dysfunction required treatment with invasive procedures, such as exchange transfusion or dialysis.

Methodological limitations of these postmarketing studies and reports include lack of a control group; limited information regarding dose, duration, and timing of drug exposure; and concomitant use of other medications. These limitations preclude establishing a reliable estimate of the risk of adverse fetal and neonatal outcomes with maternal NSAID use. Because the published safety data on neonatal outcomes involved mostly preterm infants, the generalizability of certain reported risks to the full-term infant exposed to NSAIDs through maternal use is uncertain.

Esomeprazole

Esomeprazole is the S-isomer of omeprazole. Four epidemiological studies compared the frequency of congenital abnormalities among infants born to women who used omeprazole during pregnancy with the frequency of abnormalities among infants of women exposed to H2-receptor antagonists or other controls.

A population-based retrospective cohort epidemiological study from the Swedish Medical Birth Registry, covering approximately 99% of pregnancies, from 1995 to 99, reported on 955 infants (824 exposed during the first trimester with 39 of these exposed beyond first trimester, and 131 exposed after the first trimester) whose mothers used omeprazole during pregnancy. The number of infants exposed in utero to omeprazole that had any malformation, low birth weight, low Apgar score, or hospitalization was similar to the number observed in this population. The number of infants born with ventricular septal defects and the number of stillborn infants was slightly higher in the omeprazole-exposed infants than the expected number in this population.

A population-based retrospective cohort study covering all live births in Denmark from 1996 to 2009, reported on 1,800 live births whose mothers used omeprazole during the first trimester of pregnancy and 837, 317 live births whose mothers did not use any proton pump inhibitor. The overall rate of birth defects in infants born to mothers with first trimester exposure to omeprazole was 2.9% and 2.6% in infants born to mothers not exposed to any proton pump inhibitor during the first trimester.

A retrospective cohort study reported on 689 pregnant women exposed to either H2-blockers or omeprazole in the first trimester (134 exposed to omeprazole) and 1,572 pregnant women unexposed to either during the first trimester. The overall malformation rate in offspring born to mothers with first trimester exposure to omeprazole, an H2-blocker, or were unexposed was 3.6%, 5.5%, and 4.1% respectively.

A small prospective observational cohort study followed 113 women exposed to omeprazole during pregnancy (89% first trimester exposures). The reported rate of major congenital malformations was 4% in the omeprazole group, 2% in controls exposed to non-teratogens, and 2.8% in disease-paired controls. Rates of spontaneous and elective abortions, preterm deliveries, gestational age at delivery, and mean birth weight were similar among the groups.

Several studies have reported no apparent adverse short-term effects on the infant when single dose oral or intravenous omeprazole was administered to over 200 pregnant women as premedication for cesarean section under general anesthesia.

Animal Data

There are no reproduction studies in animals with naproxen and esomeprazole magnesium delayed-release tablets, a combination of naproxen and esomeprazole.

Naproxen

Reproduction studies with naproxen administered during the period of organogenesis have been performed in rats at 20 mg/kg/day (0.13 times the maximum recommended human daily dose of 1500 mg/day based on body surface area comparison) rabbits at 20 mg/kg/day (0.26 times the maximum recommended human daily dose, based on body surface area comparison), and mice at 170 mg/kg/day (0.56 times the maximum recommended human daily dose based on body surface area comparison) with no evidence of harm to the fetus due to the drug.

Esomeprazole

No effects on embryo-fetal development were observed in reproduction studies with esomeprazole magnesium in rats at oral doses up to 280 mg/kg/day (about 68 times an oral human dose of 40 mg on a body surface area basis) or in rabbits at oral doses up to 86 mg/kg/day (about 42 times an oral human dose of 40 mg esomeprazole or 40 mg omeprazole on a body surface area basis) administered during organogenesis and have revealed no evidence of harm to the fetus due to esomeprazole magnesium.

A pre-and postnatal developmental toxicity study in rats with additional endpoints to evaluate bone development were performed with esomeprazole magnesium at oral doses of 14 to 280 mg/kg/day (about 3.4 to 68 times a daily human dose of 40 mg on a body surface area basis). Neonatal/early postnatal (birth to weaning) survival was decreased at doses equal to or greater than 138 mg/kg/day (about 34 times an oral human dose of 40 mg on a body surface area basis). Body weight and body weight gain were reduced and neurobehavioral or general developmental delays in the immediate post-weaning timeframe were evident at doses equal to or greater than 69 mg /kg/day (about 17 times an oral human dose of 40 mg on a body surface area basis). In addition, decreased femur length, width and thickness of cortical bone, decreased thickness of the tibial growth plate and minimal to mild bone marrow hypocellularity were noted at doses equal to or greater than 14 mg/kg/day (about 3.4 times a daily human dose of 40 mg on a body surface area basis). Physeal dysplasia in the femur was observed in offspring of rats treated with oral doses of esomeprazole magnesium at doses equal to or greater than 138 mg/kg/day (about 34 times the daily human dose of 40 mg on a body surface area basis).

Effects on maternal bone were observed in pregnant and lactating rats in the pre-and postnatal toxicity study when esomeprazole magnesium was administered at oral doses of 14 to 280 mg /kg/day (about 3.4 to 68 times an oral human dose of 40 mg on a body surface area basis). When rats were dosed from gestational day 7 through weaning on postnatal day 21, a statistically significant decrease in maternal femur weight of up to 14% (as compared to placebo treatment) was observed at doses equal to or greater than 138 mg/kg/day (about 34 times an oral human dose of 40 mg on a body surface area basis).

A pre-and postnatal development study in rats with esomeprazole strontium (using equimolar doses compared to esomeprazole magnesium study) produced similar results in dams and pups as described above. A follow up developmental toxicity study in rats with further time points to evaluate pup bone development from postnatal day 2 to adulthood was performed with esomeprazole magnesium at oral doses of 280 mg/kg/day (about 68 times an oral human dose of 40 mg on a body surface area basis) where esomeprazole administration was from either gestational day 7 or gestational day 16 until parturition. When maternal administration was confined to gestation only, there were no effects on bone physeal morphology in the offspring at any age.

8.2 Lactation

Risk Summary

Limited data from published literature report that naproxen anion has been found in the milk of lactating women at a concentration equivalent to approximately 1% of maximum naproxen concentration in plasma. Esomeprazole is the S-isomer of omeprazole and limited data from published literature suggest omeprazole may be present in human milk. There is no information on the effects of naproxen or omeprazole on the breastfed infant or on milk production. The developmental and health benefits of breastfeeding should be considered along with the mother’s clinical need for naproxen and esomeprazole magnesium delayed-release tablets and any potential adverse effects on the breastfed infant from the drug or from the underlying maternal condition.

8.3 Females and Males of Reproductive Potential

Infertility

Females

Based on the mechanism of action, the use of prostaglandin-mediated NSAIDs, including naproxen and esomeprazole magnesium delayed-release tablets, may delay or prevent rupture of ovarian follicles that may lead to reversible infertility in some women. Small studies in women treated with NSAIDs have also shown a reversible delay in ovulation. Published animal studies have shown that administration of prostaglandin synthesis inhibitors have the potential to disrupt prostaglandin-mediated follicular rupture required for ovulation. Consider withdrawal of NSAIDs, including naproxen and esomeprazole magnesium delayed-release tablets, in women who have difficulties conceiving or who are undergoing investigation of infertility.

8.4 Pediatric Use

The safety and effectiveness of naproxen and esomeprazole magnesium delayed-release tablets have been established in adolescent patients 12 years of age and older weighing at least 38 kg for the symptomatic relief of JIA and to decrease the risk of developing naproxen-associated gastric ulcers. Use of naproxen and esomeprazole magnesium delayed-release tablets in this age group is based on extrapolation of adequate and well-controlled studies in adults and supported by a 6 month safety study including pharmacokinetic assessment of naproxen and esomeprazole magnesium in 36 adolescent patients with JIA. Based on the limited data, the plasma naproxen and plasma esomeprazole concentrations were found to be within the range to that observed to those found in healthy adults. The safety profile of naproxen and esomeprazole magnesium delayed-release tablets in adolescent patients with JIA was similar to adults with RA.

The safety and effectiveness of naproxen and esomeprazole magnesium delayed-release tablets in pediatric patients less than 12 years of age or less than 38 kg with JIA have not been established.

Juvenile Animal Data

In a juvenile rat toxicity study, esomeprazole was administered with both magnesium and strontium salts at oral doses about 34 to 68 times a daily human dose of 40 mg based on body surface area. Increases in death were seen at the high dose, and at all doses of esomeprazole, there were decreases in body weight, body weight gain, femur weight and femur length, and decreases in overall growth [see Nonclinical Toxicology (13.2)].

8.5 Geriatric Use

Elderly patients, compared to younger patients, are at greater risk for NSAID-associated serious cardiovascular, gastrointestinal, and/or renal adverse reactions. If the anticipated benefit for the elderly patient outweighs these potential risks, start dosing at the low end of the dosing range, and monitor patients for adverse effects [see Warnings and Precautions (5.1, 5.2, 5.3, 5.6, 5.14)].

Of the total number of patients who received naproxen and esomeprazole magnesium delayed-release tablets (n=1,157) in clinical trials, 387 were greater than or equal to 65 years of age, of which 85 patients were 75 years and over. No meaningful differences in efficacy or safety were observed between these subjects and younger subjects [see Adverse Reactions (6)].

Studies indicate that although total plasma concentration of naproxen is unchanged, the unbound plasma fraction of naproxen is increased in the elderly. Caution is advised when high doses are required and some adjustment of dosage may be required in elderly patients. As with other drugs used in the elderly, it is prudent to use the lowest effective dose [see Dosage and Administration (2), Clinical Pharmacology (12.3)].

Experience indicates that geriatric patients may be particularly sensitive to certain adverse effects of NSAIDs. Elderly or debilitated patients seem to tolerate peptic ulceration or bleeding less well when these events do occur. Most spontaneous reports of fatal GI events are in the geriatric population [see Warnings and Precautions (5.2)].

Naproxen and its metabolites are known to be substantially excreted by the kidney, and the risk of adverse reactions to this drug may be greater in patients with impaired renal function. Because elderly patients are more likely to have decreased renal function, care should be taken in dose selection, and it may be useful to monitor renal function. Geriatric patients may be at a greater risk for the development of a form of renal toxicity precipitated by reduced prostaglandin formation during administration of NSAIDs [see Warnings and Precautions (5.6)].

8.6 Hepatic Impairment

Naproxen and esomeprazole magnesium delayed-release tablets should be avoided in patients with severe hepatic impairment because naproxen may increase the risk of renal failure or bleeding and esomeprazole doses should not exceed 20 mg daily in these patients [see Dosage and Administration (2), Warnings and Precautions (5.3), Clinical Pharmacology (12.3)].

8.7 Renal Impairment

Naproxen-containing products, including naproxen and esomeprazole magnesium delayed-release tablets, are not recommended for use in patients with advanced renal disease [see Dosage and Administration (2), Warnings and Precautions (5.6)].

10 OVERDOSAGE

There is no clinical data on overdosage with naproxen and esomeprazole magnesium delayed-release tablets.

Overdosage of naproxen:

Symptoms following acute NSAID overdosages have been typically limited to lethargy, drowsiness, nausea, vomiting, and epigastric pain, which have been generally reversible with supportive care. Gastrointestinal bleeding has occurred. Hypertension, acute renal failure, respiratory depression, and coma have occurred but were rare [see Warnings and Precautions (5.1, 5.2, 5.4, 5.6)].

A few patients have experienced seizures, but it is not clear whether or not these were drug-related. It is not known what dose of the drug would be life threatening. The oral LD50 of the drug is 500 mg/kg in rats, 1200 mg/kg in mice, 4000 mg/kg in hamsters and greater than 1000 mg/kg in dogs. In animals 0.5 g/kg of activated charcoal was effective in reducing plasma levels of naproxen.

Manage patients with symptomatic and supportive care following an NSAID overdosage. There are no specific antidotes. Hemodialysis does not decrease the plasma concentration of naproxen because of the high degree of its protein binding. Consider emesis and/or activated charcoal (60 to 100 grams in adults, 1 to 2 grams per kg of body weight in pediatric patients) and/or osmotic cathartic in symptomatic patients seen within four hours of ingestion or in patients with a large overdosage (5 to 10 times the recommended dosage). Forced diuresis, alkalinization of urine, hemodialysis, or hemoperfusion may not be useful due to high protein binding.

Overdosage of esomeprazole:

A single oral dose of esomeprazole at 510 mg/kg (about 124 times the human dose on a body surface area basis) was lethal to rats. The major signs of acute toxicity were reduced motor activity, changes in respiratory frequency, tremor, ataxia, and intermittent clonic convulsions. The symptoms described in connection with deliberate esomeprazole overdose (limited experience of doses in excess of 240 mg/day) are transient. Single doses of 80 mg of esomeprazole were uneventful. Reports of overdosage with omeprazole in humans may also be relevant. Doses ranged up to 2,400 mg (120 times the usual recommended clinical dose). Manifestations were variable, but included confusion, drowsiness, blurred vision, tachycardia, nausea, diaphoresis, flushing, headache, dry mouth, and other adverse reactions similar to those seen in normal clinical experience (see omeprazole package insert -Adverse Reactions). No specific antidote for esomeprazole is known. Since esomeprazole is extensively protein bound, it is not expected to be removed by dialysis. In the event of overdosage, treatment should be symptomatic and supportive.

If over-exposure occurs, call your Poison Control Center at 1-800-222-1222 for current information on the management of poisoning or overdosage.

11 DESCRIPTION

The active ingredients of naproxen and esomeprazole magnesium delayed-release tablets are naproxen, USP which is an NSAID and esomeprazole magnesium, USP which is a Proton Pump Inhibitor (PPI).

Naproxen and esomeprazole magnesium delayed-release tablets are combination of a nonsteroidal anti-inflammatory drug and a PPI available as an oval, yellow, multi-layer, delayed-release tablet combining an enteric-coated naproxen core and an immediate-release esomeprazole magnesium layer surrounding the core.

Each strength contains either 375 mg of naproxen, USP and 20 mg of esomeprazole (equivalent to 21.75 mg esomeprazole magnesium dihydrate) or 500 mg of naproxen and 20 mg of esomeprazole (equivalent to 21.75 mg esomeprazole magnesium dihydrate) for oral administration. The inactive ingredients are microcrystalline cellulose, croscarmellose sodium, povidone, colloidal silicon dioxide, magnesium stearate, methacrylic acid and ethyl acrylate copolymer, talc, triethy citrate, hypromellose, macrogol, sodium lauryl sulfate, magnesium oxide, polyethylene glycol, ferric oxide yellow. The imprinting ink contains shellac glaze, black iron oxide, propylene glycol, ammonium hydroxide.
The chemical name for naproxen, USP is (S)-2-(6-Methoxy-naphth-2-yl) propionic acid. Naproxen, USP has the following structure:

Naproxen, USP has a molecular weight of 230.26 and a molecular formula of C14H14O3.

Naproxen, USP is an odorless, white to off-white crystalline powder. It is practically insoluble in water and soluble in ethanol and methanol. The octanol/water partition coefficient of naproxen is 3.18.

The chemical name for esomeprazole is Magnesium bis [5-methoxy-2-[(S)-[(4-methoxy-3,5-dimethylpyridin-2-yl)methyl]sulphinyl]-1Hbenzimidazol-1- ide]dihydrate. Esomeprazole is the S-isomer of omeprazole, which is a mixture of the S-and R-isomers. Its molecular formula is C34H36N6O6S2Mg.2H2O with molecular weight of 749.15 as a dihydrate and 713.15 on an anhydrous basis. The structural formula is:

The magnesium salt is a white to slightly colored powder. It contains 2 moles of water of solvation and is slightly soluble in methanol, practically insoluble in water and heptane.

The stability of esomeprazole magnesium, USP is a function of pH; it rapidly degrades in acidic media, but it has acceptable stability under alkaline conditions. At pH 6.8 (buffer), the half-life of the magnesium salt is about 19 hours at 25°C and about 8 hours at 37°C.

12 CLINICAL PHARMACOLOGY

12.1 Mechanism of Action

Naproxen and esomeprazole magnesium delayed-release tablets consist of an immediate-release esomeprazole magnesium layer and an enteric-coated naproxen core. As a result, esomeprazole is released first in the stomach, prior to the dissolution of naproxen in the small intestine. The enteric coating prevents naproxen release at pH levels below 5.5.

The mechanism of action of the naproxen anion, like that of other NSAIDs, is not completely understood but inhibition of cyclooxygenase (COX-1 and COX-2).

Naproxen and esomeprazole magnesium delayed-release tablets have analgesic, anti-inflammatory, and antipyretic properties contributed by the naproxen component. Naproxen is a potent inhibitor of prostaglandin synthesis in vitro. Naproxen concentrations reached during therapy have produced in vivo effects. Prostaglandins sensitize afferent nerves and potentiate the action of bradykinin in inducing pain in animal models. Prostaglandins are mediators of inflammation. Because naproxen is an inhibitor of prostaglandin synthesis, its mode of action may be due to an increase of prostaglandins in peripheral tissues.

Esomeprazole is a proton pump inhibitor that suppresses gastric acid secretion by specific inhibition of the H^+/K^+-ATPase in the gastric parietal cell. Esomeprazole is protonated and converted in the acidic compartment of the parietal cell forming the active inhibitor, the achiral sulphenamide. By acting specifically on the proton pump, esomeprazole blocks the final step in acid production, thus reducing gastric acidity. This effect is dose-related up to a daily dose of 20 mg to 40 mg and leads to inhibition of gastric acid secretion.

12.2 Pharmacodynamics

Interaction with Aspirin
In a healthy volunteer study, 10 days of concomitant administration of naproxen 220 mg once-daily with low-dose immediate-release aspirin (81 mg) showed an interaction with the antiplatelet activity of aspirin as measured by % serum thromboxane B2 inhibition at 24 hours following the day 10 dose [98.7% (aspirin alone) vs 93.1% (naproxen and aspirin)]. The interaction was
observed even following discontinuation of naproxen on day 11 (while aspirin dose was continued) but normalized by day 13. In the same study, the interaction was greater when naproxen was administered 30 minutes prior to aspirin [98.7% vs 87.7%] and minimal when aspirin was administered 30 minutes prior to naproxen [98.7% vs 95.4%].

Following administration of naproxen 220 mg twice-daily with low-dose immediate-release aspirin (first naproxen dose given 30 minutes prior to aspirin), the interaction was minimal at 24 h following day 10 dose [98.7% vs 95.7%]. However, the interaction was more prominent after discontinuation of naproxen (washout) on day 11 [98.7% vs 84.3%] and did not normalize completely by day 13 [98.5% vs 90.7%] [see Drug Interactions (7)].

Antisecretory Activity

The effect of naproxen and esomeprazole magnesium delayed-release tablets on intragastric pH was determined in 25 healthy volunteers in one study. Three naproxen and esomeprazole magnesium delayed-release tablets combinations (naproxen 500 mg combined with either esomeprazole 10 mg, 20 mg, or 30 mg) were administered twice daily over 9 days. The results are shown in the following table:

Table 5: Effect on Intragastric pH on Day 9 (N=25)
 | Naproxen 500 mg combined with esomeprazole
 | 10 mg | 20 mg | 30 mg
% Time Gastric pH >4† | 41.1 (3.0) | 71.5 (3.0) | 76.8 (3.0)
Coefficient of variation | 55% | 18% | 16%
†Gastric pH was measured over a 24-hour period
LS Mean (SE)

Serum Gastrin Effects

The effect of esomeprazole on serum gastrin concentrations was evaluated in approximately 2,700 patients in clinical trials up to 8 weeks and in over 1,300 patients for up to 6 to12 months. The mean fasting gastrin level increased in a dose-related manner. This increase reached a plateau within two to three months of therapy and returned to baseline levels within four weeks after discontinuation of therapy.

Increased gastrin causes enterochromaffin-like cell hyperplasia and increased serum Chromogranin A (CgA) levels. The increased CgA levels may cause false positive results in diagnostic investigations for neuroendocrine tumors. Healthcare providers should temporarily stop esomeprazole treatment at least 14 days before assessing CgA levels and consider repeating the test if initial CgA levels are high.

Enterochromaffin-like (ECL) Cell Effects

In over 1,000 patients treated with esomeprazole (10, 20 or 40 mg/day) up to 6 to12 months, the prevalence of ECL cell hyperplasia increased with time and dose. No patient developed ECL cell carcinoids, dysplasia, or neoplasia in the gastric mucosa.

Endocrine Effects

Esomeprazole had no effect on thyroid function when given in oral doses of 20 or 40 mg for 4 weeks. Other effects of esomeprazole on the endocrine system were assessed using omeprazole studies. Omeprazole given in oral doses of 30 or 40 mg for 2 to 4 weeks had no effect on carbohydrate metabolism, circulating levels of parathyroid hormone, cortisol, estradiol, testosterone, prolactin, cholecystokinin or secretin.

Effects on Gastrointestinal Microbial Ecology

Decreased gastric acidity due to any means including proton pump inhibitors, increases gastric counts of bacteria normally present in the gastrointestinal tract. Treatment with proton pump inhibitors may lead to slightly increased risk of gastrointestinal infections such as Salmonella and Campylobacter and, in hospitalized patients, possibly also Clostridium difficile.

12.3 Pharmacokinetics

Absorption

Naproxen

At steady state following administration of naproxen and esomeprazole magnesium delayed-release tablets twice daily, peak plasma concentrations of naproxen are reached on average 3 hours following both the morning and the evening dose.

Bioequivalence between naproxen and esomeprazole magnesium delayed-release tablets and enteric-coated naproxen, based on both area under the plasma concentration-time curve (AUC) and maximum plasma concentration (Cmax) of naproxen, has been demonstrated for both the 375 mg and 500 mg doses.

Naproxen is absorbed from the gastrointestinal tract with an in vivo bioavailability of 95%.

Steady-state levels of naproxen are reached in 4 to 5 days.

Esomeprazole

Following administration of naproxen and esomeprazole magnesium delayed-release tablets twice daily, esomeprazole is rapidly absorbed with peak plasma concentration reached within on average, 0.43 to 1.2 hours, following the morning and evening dose on both the first day of administration and at steady state. The peak plasma concentrations of esomeprazole are higher at steady state compared to on first day of dosing of naproxen and esomeprazole magnesium delayed-release tablets.
Figure 1 represents the pharmacokinetics of naproxen and esomeprazole following administration of naproxen and esomeprazole magnesium delayed-release tablets 500 mg/20 mg.

Figure 1: Mean plasma concentrations of naproxen and esomeprazole following single dose administration of naproxen and esomeprazole magnesium delayed-release tablets (500mg/20 mg)

Food Effect

Administration of naproxen and esomeprazole magnesium delayed-release tablets together with high-fat food in healthy volunteers does not affect the extent of absorption of naproxen but significantly prolongs tmax by 10 hours and decreases peak plasma concentration (Cmax) by about 12%.

Administration of naproxen and esomeprazole magnesium delayed-release tablets together with high-fat food in healthy volunteers delays tmax of esomeprazole by 1 hour and significantly reduces the extent of absorption, resulting in 52% and 75% reductions of area under the plasma concentration versus time curve (AUC) and peak plasma concentration (Cmax), respectively.

Administration of naproxen and esomeprazole magnesium delayed-release tablets 30 minutes before high-fat food intake in healthy volunteers does not affect the extent of absorption of naproxen but delays the absorption by about 4 hours and decreases peak plasma concentration (Cmax) by about 17%, but has no significant effect on the rate or extent of esomeprazole absorption compared to administration under fasted conditions [see Dosage and Administration (2)].

Administration of naproxen and esomeprazole magnesium delayed-release tablets 60 minutes before high-fat food intake in healthy volunteers has no effect on the rate and extent of naproxen absorption; however, increases the esomeprazole AUC by 25% and Cmax by 50% compared to administration under fasted conditions. This increase in esomeprazole Cmax does not raise a safety issue since the approved dosing regimen of esomeprazole at 40 mg QD would result in higher Cmax [see Dosage and Administration (2)].

Therefore, naproxen and esomeprazole magnesium delayed-release tablets should be taken at least 30 minutes before the meal.

Distribution

Naproxen

Naproxen has a volume of distribution of 0.16 L/kg. At therapeutic levels naproxen is greater than 99% albumin-bound. At doses of naproxen greater than 500 mg/day there is less than proportional increase in plasma levels due to an increase in clearance caused by saturation of plasma protein binding at higher doses (average trough Css 36.5, 49.2 and 56.4 mg/L with 500, 1000 and 1500 mg daily doses of naproxen, respectively). The naproxen anion has been found in the milk of lactating women at a concentration equivalent to approximately 1% of maximum naproxen concentration in plasma [see Use in Specific Populations (8.2)].

Esomeprazole

The apparent volume of distribution at steady state in healthy subjects is approximately 16L. Esomeprazole is 97% plasma protein bound.

Elimination

Metabolism

Naproxen

Naproxen is extensively metabolized in the liver by the cytochrome P450 system (CYP), CYP2C9 and CYP1A2, to 6-0-desmethyl naproxen. Neither the parent drug nor the metabolites induce metabolizing enzymes. Both naproxen and 6-0-desmethyl naproxen are further metabolized to their respective acylglucuronide conjugated metabolites. Consistent with the half-life of naproxen, the area under the plasma concentration time curve increases with repeated dosing of naproxen and esomeprazole magnesium delayed-release tablets twice daily.

Esomeprazole

Esomeprazole is extensively metabolized in the liver by the CYP enzyme system. The major part of the metabolism of esomeprazole is dependent on the polymorphic CYP2C19, responsible for the formation of the hydroxyl-and desmethyl metabolites of esomeprazole. The remaining part is dependent on another specific isoform CYP3A4, responsible for the formation of esomeprazole sulphone, the main metabolite in plasma. The major metabolites of esomeprazole have no effect on gastric acid secretion.

The area under the plasma esomeprazole concentration-time curve increases with repeated administration of naproxen and esomeprazole magnesium delayed-release tablets. This increase is dose-dependent and results in a non-linear dose-AUC relationship after repeated administration. An increased absorption of esomeprazole with repeated administration of naproxen and esomeprazole magnesium delayed-release tablets probably also contributes to the time-and dose-dependency.

Excretion

Naproxen

Following administration of naproxen and esomeprazole magnesium delayed-release tablets twice daily, the mean elimination half-life for naproxen is approximately 15 hours following the evening dose, with no change with repeated dosing.

The clearance of naproxen is 0.13 mL/min/kg. Approximately 95% of the naproxen from any dose is excreted in the urine, primarily as naproxen (less than 1%), 6-0-desmethyl naproxen (less than 1%) or their conjugates (66% to 92%). Small amounts, 3% or less of the administered dose, are excreted in the feces. In patients with renal failure, metabolites may accumulate [see Warnings and Precautions (5.6)].

Esomeprazole

Following administration of naproxen and esomeprazole magnesium delayed-release tablets twice daily, the mean elimination half-life of esomeprazole is approximately 1 hour following both the morning and evening dose on day 1, with a slightly longer elimination half-life at steady state (1.2 hours to 1.5 hours).

Almost 80% of an oral dose of esomeprazole is excreted as metabolites in the urine, the remainder in the feces. Less than 1% of the parent drug is found in the urine.

Specific Populations

Geriatric Patients

There is no specific data on the pharmacokinetics of naproxen and esomeprazole magnesium delayed-release tablets in patients over age 65.

Studies indicate that although total plasma concentration of naproxen is unchanged, the unbound plasma fraction of naproxen is increased in the elderly, although the unbound fraction is less than 1% of the total naproxen concentration. Unbound trough naproxen concentrations in elderly subjects have been reported to range from 0.12% to 0.19% of total naproxen concentration, compared with 0.05% to 0.075% in younger subjects. The clinical significance of this finding is unclear, although it is possible that the increase in free naproxen concentration could be associated with an increase in the rate of adverse events per a given dosage in some elderly patients [see Adverse Reactions (6) and Use in Specific Populations (8.5)].

The AUC and Cmax values of esomeprazole were slightly higher (25% and 18%, respectively) in the elderly as compared to younger subjects at steady state. Dosage adjustment for the esomeprazole component based on age is not necessary.

Male and Female Patients

The AUC and Cmax values of esomeprazole were slightly higher (13%) in females than in males at steady state. Dosage adjustment for the esomeprazole component based on gender is not necessary.

Racial or Ethnic Groups

Pharmacokinetic differences due to race have not been studied for naproxen.

Approximately 3% of Caucasians and 15 % to 20 % of Asians lack a functional CYP2C19 enzyme and are called poor metabolizers. In these individuals the metabolism of esomeprazole is probably mainly catalyzed by CYP3A4. After repeated once-daily administration of 40 mg esomeprazole, the mean area under the plasma concentration-time curve was approximately 100% higher in poor metabolizers than in subjects having a functional CYP2C19 enzyme (extensive metabolizers).

Patients with Renal Impairment

The pharmacokinetics of naproxen and esomeprazole magnesium delayed-release tablets or naproxen have not been determined in subjects with renal impairment.

Given that naproxen, its metabolites and conjugates are primarily excreted by the kidney, the potential exists for naproxen metabolites to accumulate in the presence of renal impairment. Elimination of naproxen is decreased in patients with severe renal impairment. Naproxen-containing products, including naproxen and esomeprazole magnesium delayed-release tablets, is not recommended for use in patients with moderate to severe and severe renal impairment (creatinine clearance less than 30 ml/min) [see Dosage and Administration (2), Warnings and Precautions (5.6), Use in Specific Populations (8.7)].

No studies have been performed with esomeprazole in patients with decreased renal function. Since the kidney is responsible for the excretion of the metabolites of esomeprazole but not for the elimination of the parent compound, the metabolism of esomeprazole is not expected to be changed in patients with impaired renal function.

Patients with Hepatic Impairment

The pharmacokinetics of naproxen and esomeprazole magnesium delayed-release tablets or naproxen have not been determined in subjects with hepatic impairment.

In patients with severe hepatic impairment, naproxen and esomeprazole magnesium delayed-release tablets should be avoided due to increase of risk of NSAID associated bleeding and/or renal failure associated with naproxen.

Chronic alcoholic liver disease and probably also other forms of cirrhosis reduce the total plasma concentration of naproxen, but the plasma concentration of unbound naproxen is increased. The implication of this finding for the naproxen component of naproxen and esomeprazole magnesium delayed-release tablets dosing is unknown but it is prudent to use the lowest effective dose.

The AUCs of esomeprazole in patients with severe hepatic impairment (Child Pugh Class C) have been shown to be 2 times to 3 times higher than in patients with normal liver function. For this reason, it has been recommended that esomeprazole doses not exceed 20 mg daily in patients with severe hepatic impairment. However, there is no dose adjustment necessary for patients with Child Pugh Class A and B for the esomeprazole component of naproxen and esomeprazole magnesium delayed-release tablets. There is no naproxen and esomeprazole magnesium delayed-release tablets dosage form that contains less than 20 mg esomeprazole for twice daily dosing [see Dosage and Administration (2), Warnings and Precautions (5.3)].

Drug Interaction Studies

Effect of Naproxen on Other Drugs

Aspirin: When NSAIDs were administered with aspirin, the protein binding of NSAIDs were reduced, although the clearance of free NSAID was not altered. The clinical significance of this interaction is not known. See Table 3 for clinically significant drug interactions of NSAIDs with aspirin [see Drug Interactions (7)].

Effect of Esomeprazole on Other Drugs

Cytochrome P 450 Interactions

Esomeprazole is extensively metabolized in the liver by CYP2C19 and CYP3A4. In vitro and in vivo studies have shown that esomeprazole is not likely to inhibit CYPs 1A2, 2A6, 2C9, 2D6, 2E1 and 3A4. No clinically relevant interactions with drugs metabolized by these CYP enzymes would be expected. Drug interaction studies have shown that esomeprazole does not have any clinically significant interactions with phenytoin, warfarin, quinidine, clarithromycin or amoxicillin.

Clopidogrel: Results from a crossover study in healthy subjects have shown a pharmacokinetic interaction between clopidogrel (300 mg loading dose/75 mg daily maintenance dose) and esomeprazole (40 mg p.o. once daily) when co-administered for 30 days. Exposure to the active metabolite of clopidogrel was reduced by 35% to 40% over this time period. Pharmacodynamic parameters were also measured and demonstrated that the change in inhibition of platelet aggregation was related to the change in the exposure to clopidogrel active metabolite [see Warnings and Precautions (5.22), Drug Interactions (7)].

Mycophenolate Mofetil: Administration of omeprazole 20 mg twice daily for 4 days and a single 1000 mg dose of MMF approximately one hour after the last dose of omeprazole to 12 healthy subjects in a cross-over study resulted in a 52% reduction in the Cmax and 23% reduction in the AUC of MPA [see Drug Interactions (7)].

Cilostazol: Omeprazole acts as an inhibitor of CYP2C19. Omeprazole, given in doses of 40 mg daily for one week to 20 healthy subjects in cross-over study, increased Cmax and AUC of cilostazol by 18% and 26% respectively. Cmax and AUC of one of its active metabolites, 3,4-dihydrocilostazol, which has 4 to 7 times the activity of cilostazol, were increased by 29% and 69% respectively [see Drug Interactions (7)].

Nelfinavir: Following multiple doses of nelfinavir (1250 mg, twice daily) and omeprazole (40 mg once a day), AUC was decreased by 36% and 92%, Cmax by 37% and 89% and Cmin by 39% and 75% respectively for nelfinavir and main oxidative metabolite, hydroxy-t-butylamide (M8) [see Drug Interactions (7)].

Atazanavir: Following multiple doses of atazanavir (400 mg, once a day) and omeprazole (40 mg, once a day, 2 hr before atazanavir), AUC was decreased by 94%, Cmax by 96%, and Cmin by 95% [see Drug Interactions (7)].

Saquinavir: Elevated serum levels have been reported with an increase in AUC by 82% in Cmax by 75% and in Cmin by 106% following multiple dosing of saquinavir/ritonavir (1000/100 mg) twice a day for 15 days with omeprazole 40 mg once a day co-administered on days 11 to 15 [see Drug Interactions (7)].

Diazepam: Co-administration of esomeprazole 30 mg and diazepam, a CYP2C19 substrate, resulted in a 45% decrease in clearance of diazepam [see Drug Interactions (7)].

Digoxin: Concomitant administration of omeprazole 20 mg once daily and digoxin in healthy subjects increased the bioavailability of digoxin by 10% (30% in two subjects) [see Drug Interactions (7)].

Effect of Other Drugs on Esomeprazole

Because esomeprazole is metabolized by CYP2C19 and CYP3A4, inducers and inhibitors of these enzymes may potentially alter exposure of esomeprazole.

St. John’s Wort: In a cross-over study in 12 healthy male subjects, St. John’s Wort (300 mg three times daily for 14 days) significantly decreased the systemic exposure of omeprazole in CYP2C19 poor metabolizers (Cmax and AUC decreased by 37.5% and 37.9%, respectively) and extensive metabolizers (Cmax and AUC decreased by 49.6% and 43.9%, respectively) [see Warnings and Precautions (5.25), Drug Interactions (7)].

Voriconazole: Concomitant administration of omeprazole and voriconazole (a combined inhibitor of CYP2C19 and CYP3A4) resulted in more than doubling of the omeprazole exposure. When voriconazole (400 mg every 12 hours for one day, followed by 200 mg once daily for 6 days) was given with omeprazole (40 mg once daily for 7 days) to healthy subjects, the steady-state Cmax and AUC0-24 of omeprazole significantly increased: an average of 2 times (90% CI: 1.8, 2.6) and 4 times (90% CI: 3.3, 4.4), respectively, as compared to when omeprazole was given without voriconazole [see Drug Interactions (7)].

13 NONCLINICAL TOXICOLOGY

13.1 Carcinogenesis, Mutagenesis, and Impairment of Fertility

Carcinogenesis

Naproxen

A 2-year study was performed in rats to evaluate the carcinogenic potential of naproxen at rat doses of 8, 16, and 24 mg/kg/day (0.05, 0.1, and 0.16 times the maximum recommended human daily dose of 1500 mg/day based on a body surface area comparison). The maximum dose used was 0.28 times the highest recommended human dose. No evidence of tumorigenicity was found.

Esomeprazole

The carcinogenic potential of esomeprazole was assessed using omeprazole studies, of which esomeprazole is an enantiomer. In two 24-month oral carcinogenicity studies in rats, omeprazole at daily doses of 1.7, 3.4, 13.8, 44 and 140.8 mg/kg/day (about 0.41 to 34.2 times the human dose of 40 mg/day expressed on a body surface area basis) produced gastric ECL cell carcinoids in a dose-related manner in both male and female rats; the incidence of this effect was markedly higher in female rats, which had higher blood levels of omeprazole. Gastric carcinoids seldom occur in the untreated rat. In addition, ECL cell hyperplasia was present in all treated groups of both sexes. In one of these studies, female rats were treated with 13.8 mg omeprazole/kg/day (about 3.36 times the human dose of 40 mg/day on a body surface area basis) for 1 year, then followed for an additional year without the drug. No carcinoids were seen in these rats. An increased incidence of treatment-related ECL cell hyperplasia was observed at the end of 1 year (94% treated vs 10% controls). By the second year the difference between treated and control rats was much smaller (46% vs 26%) but still showed more hyperplasia in the treated group. Gastric adenocarcinoma was seen in one rat (2%). No similar tumor was seen in male or female rats treated for 2 years. For this strain of rat, no similar tumor has been noted historically, but a finding involving only one tumor is difficult to interpret. A 78-week mouse carcinogenicity study of omeprazole did not show increased tumor occurrence, but the study was not conclusive.

Mutagenesis

Esomeprazole was negative in the Ames mutation test, in the in vivo rat bone marrow cell chromosome aberration test, and the in vivo mouse micronucleus test. Esomeprazole, however, was positive in the in vitro human lymphocyte chromosome aberration test. Omeprazole was positive in the in vitro human lymphocyte chromosome aberration test, the in vivo mouse bone marrow cell chromosome aberration test, and the in vivo mouse micronucleus test.

Impairment of Fertility

The potential effects of esomeprazole on fertility and reproductive performance were assessed using omeprazole studies. Omeprazole at oral doses up to 138 mg/kg/day in rats (about 33.6 times the human dose of 40 mg/day on a body surface area basis) was found to have no effect on reproductive performance of parental animals.

Studies to evaluate the impact of naproxen on male or female fertility have not been completed.

13.2 Animal Toxicology and/or Pharmacology

Naproxen

Reproduction studies have been performed in rats at 20 mg/kg/day (125 mg/m^2/day, 0.23 times the maximum recommended human dose), rabbits at 20 mg/kg/day (220 mg/m^2/day, 0.27 times the maximum recommended human dose), and mice at 170 mg/kg/day (510 mg/m^2/day, 0.28 times the maximum recommended human dose) with no evidence of impaired fertility or harm to the fetus due to the drug. However, animal reproduction studies are not always predictive of human response.

Esomeprazole – Reproduction Studies

Reproduction studies have been performed in rats at oral doses up to 280 mg/kg/day (about 68 times an oral human dose of 40 mg on a body surface area basis) and in rabbits at oral doses up to 86 mg/kg/day (about 42 times an oral human dose of 40 mg on a body surface area basis) and have revealed no evidence of impaired fertility or harm to the fetus due to esomeprazole [see Use in Specific Populations (8.1)].

Esomeprazole – Juvenile Animal Data

A 28-day toxicity study with a 14-day recovery phase was conducted in juvenile rats with esomeprazole magnesium at doses of 70 to 280 mg /kg/day (about 17 to 68 times a daily oral human dose of 40 mg on a body surface area basis). An increase in the number of deaths at the high dose of 280 mg /kg/day was observed when juvenile rats were administered esomeprazole magnesium from postnatal day 7 through postnatal day 35. In addition, doses equal to or greater than 140 mg/kg/day (about 34 times a daily oral human dose of 40 mg on a body surface area basis), produced treatment-related decreases in body weight (approximately 14%) and body weight gain, decreases in femur weight and femur length, and affected overall growth. Comparable findings described above have also been observed in this study with another esomeprazole salt, esomeprazole strontium, at equimolar doses of esomeprazole.

14 CLINICAL STUDIES

Two randomized, multi-center, double-blind trials (Study 1 and Study 2) compared the incidence of gastric ulcer formation in 428 patients taking naproxen and esomeprazole magnesium delayed-release tablets and 426 patients taking enteric-coated naproxen. Subjects were at least 18 years of age with a medical condition expected to require daily NSAID therapy for at least 6 months, and, if less than 50 years old, with a documented history of gastric or duodenal ulcer within the past 5 years. The majority of patients were female (67%), white (86%). The majority of patients were 50 years to 69 years of age (83%). Approximately one quarter were on low-dose aspirin.

Studies 1 and 2 showed that naproxen and esomeprazole magnesium delayed-release tablets given as 500 mg/20 mg twice daily statistically significantly reduced the 6-month cumulative incidence of gastric ulcers compared to enteric coated naproxen 500 mg twice daily (see Table 6).

Approximately a quarter of the patients in Studies 1 and 2 were taking concurrent low-dose aspirin (less than or equal to 325 mg daily). The results for this subgroup analysis in patients who used aspirin were consistent with the overall findings of the study.

The results at one month, three months, and six months are presented in Table 6.

Table 6 – Cumulative Observed Incidence of Gastric Ulcers at 1, 3 and 6 Months
 | Study 1 |  | Study 2
 | Naproxen and Esomeprazole Magnesium Delayed-Release Tablets N=218 number (%) | EC-‑naproxen N=216 number (%) | Naproxen and Esomeprazole Magnesium Delayed-Release Tablets N=210 number (%) | EC-‑naproxen N=210 number (%)
0-1 Month | 3 (1.4) | 28 (13.0) | 4 (1.9) | 21 (10.0)
0-3 Months | 4 (1.8) | 42 (19.4) | 10 (4.8) | 37 (17.6)
0-6 Months† | 9 (4.1) | 50 (23.1) | 15 (7.1) | 51 (24.3)
†For both Studies, p less than 0.001 for treatment comparisons of cumulative GU incidence at six months.

In these trials, patients receiving naproxen and esomeprazole magnesium delayed-release tablets had a mean duration of therapy of 152 days compared to 124 days in patients receiving enteric-coated naproxen alone. A higher proportion of patients taking EC-naproxen (12%) discontinued the study due to upper GI adverse events (including duodenal ulcers) compared to naproxen and esomeprazole magnesium delayed-release tablets (4%) in both trials [see Adverse Reactions (6)].

The efficacy of naproxen and esomeprazole magnesium delayed-release tablets in treating the signs and symptoms of osteoarthritis was established in two 12-week randomized, double-blind, placebo-controlled trials in patients with osteoarthritis (OA) of the knee. In these two trials, patients were allowed to remain on low-dose aspirin for cardioprophylaxis. Naproxen and esomeprazole magnesium delayed-release tablets were given as 500 mg/20 mg twice daily. In each trial, patients receiving naproxen and esomeprazole magnesium delayed-release tablets had significantly better results compared to patients receiving placebo as measured by change from baseline of the WOMAC pain subscale and the WOMAC physical function subscale and a Patient Global Assessment Score.

Based on studies with enteric-coated naproxen, improvement in patients treated for rheumatoid arthritis was demonstrated by a reduction in joint swelling, a reduction in duration of morning stiffness, a reduction in disease activity as assessed by both the investigator and patient, and by increased mobility as demonstrated by a reduction in walking time. In patients with osteoarthritis, the therapeutic action of naproxen has been shown by a reduction in joint pain or tenderness, an increase in range of motion in knee joints, increased mobility as demonstrated by a reduction in walking time, and improvement in capacity to perform activities of daily living impaired by the disease. In patients with ankylosing spondylitis, naproxen has been shown to decrease night pain, morning stiffness and pain at rest.

16 HOW SUPPLIED/STORAGE AND HANDLING

Naproxen and esomeprazole magnesium delayed-release tablets 500 mg/20 mg are yellow colored, oval shaped, biconvex film-coated tablets with NE 500 imprinted with black ink on one side and plain on other side, supplied as:

NDC 68788-8766-3 Bottles of 30 tablets

NDC 68788-8766-6 Bottles of 60 tablets

Storage: Store at 20°C to 25°C (68°F to 77°F); excursions permitted to 15°C to 30°C (59°F to 86°F) [see USP Controlled Room Temperature]. Store in the original container and keep the bottle tightly closed to protect from moisture. Dispense in a tight container if package is subdivided.

17 PATIENT COUNSELING INFORMATION

Advise the patient to read the FDA-approved patient labeling (Medication Guide).

Inform patients, families, or caregivers of the following before initiating therapy with naproxen and esomeprazole magnesium delayed-release tablets and periodically during the course of ongoing therapy.

Cardiovascular Thrombotic Events

Advise patients to be alert for the symptoms of cardiovascular thrombotic events, including chest pain, shortness of breath, weakness, or slurring of speech, and to report any of these symptoms to their health care provider immediately [see Warnings and Precautions (5.1)].

Gastrointestinal Bleeding, Ulceration, and Perforation

Advise patients to report symptoms of ulcerations and bleeding, including epigastric pain, dyspepsia, melena, and hematemesis to their health care provider. In the setting of concomitant use of low-dose aspirin for cardiac prophylaxis, inform patients of the increased risk for and the signs and symptoms of GI bleeding [see Warnings and Precautions (5.2)].

Hepatotoxicity

Inform patients of the warning signs and symptoms of hepatotoxicity (e.g., nausea, fatigue, lethargy, pruritus, jaundice, right upper quadrant tenderness, and “flu-like” symptoms). If these occur, instruct patients to stop naproxen and esomeprazole magnesium delayed-release tablets and seek immediate medical therapy [see Warnings and Precautions (5.3)].

Heart Failure and Edema

Advise patients to be alert for the symptoms of congestive heart failure including shortness of breath, unexplained weight gain, or edema and to contact their health care provider if such symptoms occur [see Warnings and Precautions (5.5)].

Anaphylactic Reactions

Inform patients of the signs of an anaphylactic reaction (e.g., difficulty breathing, swelling of the face or throat). If these occur, patients should be instructed to seek immediate emergency help [see Contraindications (4), Warnings and Precautions (5.7)].

Serious Skin Reactions, Including DRESS

Advise patients to stop taking naproxen and esomeprazole magnesium delayed-release tablets immediately if they develop any type of rash or fever and contact their health care provider as soon as possible [see Warnings and Precautions (5.9, 5.10)].

Fetal Toxicity

Inform pregnant women to avoid use of naproxen and esomeprazole magnesium delayed-release tablets and other NSAIDs starting at 30 weeks gestation because of the risk of the premature closure of the fetal ductus arteriosus. If treatment with naproxen and esomeprazole magnesium delayed-release tablets is needed for a pregnant woman between about 20 to 30 weeks gestation, advise her that she may need to be monitored for oligohydramnios [see Warnings and Precautions (5.11) Use in Specific Populations (8.1)].

Infertility

Advise females of reproductive potential that NSAIDs, including naproxen and esomeprazole magnesium delayed-release tablets, may be associated with reversible infertility [see Use in Specific Populations (8.3)].

Gastric Malignancy

To return to their healthcare provider if they have gastric symptoms while taking naproxen and esomeprazole magnesium delayed-release tablets or after completing treatment [see Warnings and Precautions (5.17)].

Acute Tubulointerstitial Nephritis

Advise patients to report to their health care provider immediately if they experience a decrease in the amount they urinate or have blood in their urine [see Warnings and Precautions (5.18)].

Clostridium difficile-Associated Diarrhea

Advise patients to immediately report and seek care for diarrhea that does not improve. This may be a sign of Clostridium difficile associated diarrhea [see Warnings and Precautions (5.19)].

Bone Fracture

Advise patients to report any sign or symptom of osteoporosis (e.g., recent bone fracture, low bone density) to their health care provider [see Warnings and Precautions (5.20)].

Cutaneous and Systemic Lupus Erythematosus

Advise patients to immediately call their healthcare provider any new or worsening of symptoms associated with cutaneous or systemic lupus erythematosus [see Warnings and Precautions (5.21)].

Cyanocobalamin (Vitamin B-12) Deficiency

Advise patients taking naproxen and esomeprazole magnesium delayed-release tablets for long periods of time, to report to their healthcare provider if they experience weakness, tiredness, or light-headedness or rapid heartbeat and breathing or pale skin [see Warnings and Precautions (5.23)].

Hypomagnesemia and Mineral Metabolism
Advise patients to report any clinical symptoms that may be associated with hypomagnesemia, hypocalcemia, and/or hypokalemia to their healthcare provider, if they have been receiving naproxen and esomeprazole magnesium delayed-release tablets for at least 3 months. [see Warnings and Precautions (5.24)].

Drug Interactions

- Inform patients that the concomitant use of naproxen and esomeprazole magnesium delayed-release tablets with other NSAIDs or salicylates (e.g., diflunisal, salsalate) it is not recommended due to the increased risk of gastrointestinal toxicity, and little or no increase in efficacy [see Warnings and Precautions (5.16), Drug Interactions (7)]. Alert patients that NSAIDs may be present in the “over the counter” medications for treatment of colds, fever or insomnia.
- Advise patients to report to their healthcare provider if they start treatment with clopidogrel, St. John’s Wort or rifampin; or, if they take high-dose methotrexate [see Warnings and Precautions (5.22, 5.25, 5.27)].
- Inform patients not to use low-dose aspirin concomitantly with naproxen and esomeprazole magnesium delayed-release tablets until they talk to their health care provider [see Drug Interactions (7)].

Administration

- Inform patients that naproxen and esomeprazole magnesium delayed-release tablets should be swallowed whole with liquid. Tablets should not be split, chewed, crushed or dissolved. Naproxen and esomeprazole magnesium delayed-release tablets should be taken at least 30 minutes before meals [see Dosage and Administration (2)].
- Patients should be instructed that if a dose is missed, it should be taken as soon as possible. However, if the next scheduled dose is due, the patient should not take the missed dose, and should be instructed to take the next dose on time. Patients should be instructed not to take 2 doses at one time to make up for a missed dose.
- Inform patients that antacids may be used while taking naproxen and esomeprazole magnesium delayed-release tablets.

Product of India
Manufactured by:
Ajanta Pharma Limited, India
Marketed by:
Ajanta Pharma USA Inc.
Bridgewater, NJ 08807.

Repackaged By: Preferred Pharmaceuticals Inc.

#All trademarks are the properties of their respective owners

Revised: 08/2025

Medication Guide
Naproxen (na prox' en) and Esomeprazole Magnesium
(es'' oh mep' ra zole mag nee' zee um)
Delayed-Release Tablets

What is the most important information I should know about naproxen and esomeprazole magnesium delayed-release tablets?
You should take naproxen and esomeprazole magnesium delayed-release tablets exactly as prescribed, at the lowest dose possible and for the shortest time needed. Naproxen and esomeprazole magnesium delayed-release tablets may help your acid-related symptoms, but you could still have serious stomach problems. Talk with your healthcare provider.
Naproxen and esomeprazole magnesium delayed-release tablets contain naproxen, a nonsteroidal anti-inflammatory drug (NSAID) and esomeprazole magnesium, a proton pump inhibitor (PPI) medicine.
Naproxen and esomeprazole magnesium delayed-release tablets can cause serious side effects including:

- Increased risk of a heart attack or stroke that can lead to death. This risk may happen early in treatment and may increase:
  - with increasing doses of NSAIDs
  - with longer use of NSAIDs

Do not take naproxen and esomeprazole magnesium delayed-release tablets right before or after a heart surgery called a “coronary artery bypass graft (CABG).” Avoid taking naproxen and esomeprazole magnesium delayed-release tablets after a recent heart attack, unless your healthcare provider tells you to. You may have an increased risk of another heart attack if you take NSAIDs after a recent heart attack.

- Increased risk of bleeding, ulcers, and tears (perforation) of the esophagus (tube leading from the mouth to the stomach), stomach and intestines:
  - anytime during use
  - without warning symptoms
  - that may cause death

The risk of getting an ulcer or bleeding increases with:

Talk to your healthcare provider or pharmacist before using other medicines that contain NSAIDs, including low-dose aspirin, during treatment with naproxen and esomeprazole magnesium delayed-release tablets. Some NSAIDs are sold in lower doses without a prescription (over-the-counter).

- A type of kidney problem (acute tubulointerstitial nephritis). Some people who take proton pump inhibitor (PPI) medicines, including naproxen and esomeprazole magnesium delayed-release tablets, may develop a kidney problem called acute tubulointerstitial nephritis that can happen at any time during treatment with naproxen and esomeprazole magnesium delayed-release tablets. Call your healthcare provider right away if you have a decrease in the amount that you urinate or if you have blood in your urine.
- Diarrhea caused by an infection (Clostridium difficile) in your intestines. Call your healthcare provider right away if you have watery stools or stomach pain that does not go away. You may or may not have a fever.
- Bone fractures (hip, wrist, or spine). Bone fractures in the hip, wrist, or spine may happen in people who take multiple daily doses of PPI medicines and for a long period of time (a year or longer). Tell your healthcare provider if you have a bone fracture, especially in the hip, wrist, or spine.
- Certain types of lupus erythematosus. Lupus erythematosus is an autoimmune disorder (the body’s immune cells attack other cells or organs in the body). Some people who take PPI medicines, including naproxen and esomeprazole magnesium delayed-release tablets, may develop certain types of lupus erythematosus or have worsening of the lupus they already have. Call your healthcare provider right away if you have new or worsening joint pain or a rash on your cheeks or arms that gets worse in the sun.

Talk to your healthcare provider about your risk of these serious side effects.
Naproxen and esomeprazole magnesium delayed-release tablets can have other serious side effects. See “What are the possible side effects of naproxen and esomeprazole magnesium delayed-release tablets?”

What is naproxen and esomeprazole magnesium delayed-release tablets?
Naproxen and esomeprazole magnesium delayed-release tablet is a prescription medicine used in adults and adolescents, 12 years of age and older who weigh at least 84 pounds (38 kg), who need to take naproxen for relief of symptoms of arthritis and who also need to decrease the risk of developing stomach ulcers caused by naproxen.
The naproxen in naproxen and esomeprazole magnesium delayed-release tablets is used for the relief of signs and symptoms of:

- osteoarthritis, rheumatoid arthritis, and ankylosing spondylitis in adults
- juvenile idiopathic arthritis (JIA) in adolescents

The esomeprazole magnesium in naproxen and esomeprazole magnesium delayed-release tablets is used to:

- decrease the risk of developing stomach ulcers in people who are taking naproxen

It is not known if naproxen and esomeprazole magnesium delayed-release tablets are safe and effective in children less than 12 years of age or who weigh less than 84 pounds (38 kg).
You should not take a naproxen tablet and an esomeprazole magnesium tablet together instead of taking naproxen and esomeprazole magnesium delayed-release tablets, because they will not work the same way.
Studies in people who take naproxen and esomeprazole magnesium delayed-release tablets have not extended past 6 months.

Do not take naproxen and esomeprazole magnesium delayed-release tablets:

- if you are allergic to naproxen, esomeprazole magnesium, omeprazole, any other PPI medicine, or any of the ingredients in naproxen and esomeprazole magnesium delayed-release tablets. See the end of this Medication Guide for a complete list of ingredients in naproxen and esomeprazole magnesium delayed-release tablets.
- if you have had an asthma attack, hives, or other allergic reaction after taking aspirin or any other NSAIDs.
- right before or after heart bypass surgery.
- if you are taking a medicine that contains rilpivirine (Edurant, Complera, Odefsey) used to treat HIV-1 (Human Immunodeficiency Virus).

Before taking naproxen and esomeprazole magnesium delayed-release tablets, tell your healthcare provider about all of your medical conditions, including if you:

- have liver, kidney, or heart problems.
- have high blood pressure.
- have asthma.
- have low magnesium levels, low calcium levels and low potassium levels in your blood.
- have ulcerative colitis or Crohn’s disease (inflammatory bowel disease or IBD).
- are pregnant or plan to become pregnant. Taking naproxen and esomeprazole magnesium delayed-release tablets at about 20 weeks of pregnancy or later may harm your unborn baby. If you need to take naproxen and esomeprazole magnesium delayed-release tablets for more than 2 days when you are between 20 weeks and 30 weeks of pregnancy, your healthcare provider may need to monitor the amount of fluid in your womb around your baby. You should not take naproxen and esomeprazole magnesium delayed-release tablets after about 30 weeks of pregnancy.
- are breastfeeding or plan to breastfeed. The naproxen in naproxen and esomeprazole magnesium delayed-release tablets can pass into your breast milk. It is not known if naproxen and esomeprazole magnesium delayed-release tablets will harm your baby. Talk to your healthcare provider about the best way to feed your baby if you take naproxen and esomeprazole magnesium delayed-release tablets.
- are a female who can become pregnant. Naproxen and esomeprazole magnesium delayed-release tablets may be related to infertility in some women that is reversible when treatment with naproxen and esomeprazole magnesium delayed-release tablets is stopped.

Tell your healthcare provider about all of the medicines you take, including prescription and over-the-counter medicines, vitamins, and herbal supplements. Naproxen and esomeprazole magnesium delayed-release tablets and some other medicines can interact with each other and cause serious side effects. Do not start taking any new medicine without talking to your healthcare provider first. Especially tell your healthcare provider if you take:

• steroid hormones (corticosteroids)
• St. John’s Wort
• rifampin (Rifater, Rifamate, Rimactane, Rifadin)
• medicine for high blood pressure or heart problems
• a water pill (diuretic)
• aspirin
• antidepressant medicine
• medicine used to reduce the risk of blood clots, such as warfarin (Coumadin, Jantoven)
• methotrexate (Otrexup, Rasuvo, Trexall, Xatmep)
• digoxin (Lanoxin)
• clopidogrel (Plavix)

How should I take naproxen and esomeprazole magnesium delayed-release tablets?

- Take naproxen and esomeprazole magnesium delayed-release tablets exactly as prescribed by your healthcare provider.
- Take 1 naproxen and esomeprazole magnesium delayed-release tablet 2 times each day.
- Take naproxen and esomeprazole magnesium delayed-release tablets at least 30 minutes before a meal.
- Swallow naproxen and esomeprazole magnesium delayed-release tablets whole with liquid. Do not split, chew, crush or dissolve naproxen and esomeprazole magnesium delayed-release tablets.
- You may use antacids while taking naproxen and esomeprazole magnesium delayed-release tablets.
- If you forget to take your dose of naproxen and esomeprazole magnesium delayed-release tablets, take it as soon as you remember. If it is almost time for your next dose, do not take the missed dose. Take the next dose on time. Do not take 2 doses at one time to make up for a missed dose.
- If you take too much naproxen and esomeprazole magnesium delayed-release tablets, call your healthcare provider or your poison control center at 1-800-222-1222 right away or go to the nearest emergency room.

What are the possible side effects of naproxen and esomeprazole magnesium delayed-release tablets?
Naproxen and esomeprazole magnesium delayed-release tablets can cause serious side effects, including:
See “What is the most important information I should know about naproxen and esomeprazole magnesium delayed-release tablets?”

- liver problems, including liver failure.
- new or worsening high blood pressure.
- heart failure.
- kidney problems, including kidney failure.
- life-threatening allergic reactions.
- asthma attacks in people who have asthma.
- life-threatening skin reactions.
- low red blood cells (anemia).
- hiding (masking) symptoms of an infection, such as swelling and fever.

- Low vitamin B-12 levels in your body can happen in people who have taken naproxen and esomeprazole magnesium delayed-release tablets for a long time (more than 3 years). Tell your healthcare provider if you have symptoms of low vitamin B-12 levels, including shortness of breath, lightheadedness, irregular heartbeat, muscle weakness, pale skin, feeling tired, mood changes, and tingling or numbness in the arms or legs.
- Low magnesium levels in your body can happen in people who have taken naproxen and esomeprazole magnesium delayed-release tablets for at least 3 months. Tell your healthcare provider if you have symptoms of low magnesium levels, including seizures, dizziness, irregular heartbeat, jitteriness, muscle aches or weakness, and spasms of hands, feet or voice.
- Stomach growths (fundic gland polyps) People who take PPI medicines for a long time have an increased risk of developing a certain type of stomach growths called fundic gland polyps, especially after taking PPI medicines for more than 1 year.
- Severe skin reactions. Naproxen and esomeprazole magnesium delayed-release tablets can cause rare but severe skin reactions that may affect any part of your body. These serious skin reactions may need to be treated in a hospital and may be life threatening:
  - Skin rash which may have blistering, peeling or bleeding on any part of your skin (including your lips, eyes, mouth, nose, genitals, hands or feet).
  - You may also have fever, chills, body aches, shortness of breath, or enlarged lymph nodes.

Stop taking naproxen and esomeprazole magnesium delayed-release tablets and call your doctor right away. These symptoms may be the first sign of a severe skin reaction.
The most common side effects of naproxen and esomeprazole magnesium delayed-release tablets include: inflammation of the lining of the stomach and diarrhea
Get emergency help right away if you get any of the following symptoms:

- shortness of breath or trouble breathing
- chest pain
- weakness in one part or side of your body
- slurred speech
- swelling of the face or throat

Stop taking naproxen and esomeprazole magnesium delayed-release tablets and call your healthcare provider right away if you get any of the following symptoms:

- nausea
- more tired or weaker than usual
- diarrhea
- itching
- your skin or eyes look yellow
- indigestion or stomach pain
- flu-like symptoms
- vomit blood
- there is blood in your bowel movement or it is black and sticky like tar
- unusual weight gain
- skin rash or blisters with fever
- swelling of the arms, legs, hands, and feet

If you take too much naproxen and esomeprazole magnesium delayed-release tablets, call your healthcare provider or get medical help right away.
These are not all the possible side effects of naproxen and esomeprazole magnesium delayed-release tablets. Call your doctor for medical advice about side effects. You may report side effects to FDA at 1-800-FDA-1088.

How should I store naproxen and esomeprazole magnesium delayed-release tablets?

- Store naproxen and esomeprazole magnesium delayed-release tablets at room temperature between 68ºF to 77ºF (20ºC to 25ºC).
- Store naproxen and esomeprazole magnesium delayed-release tablets in the original container.
- Keep the bottle of naproxen and esomeprazole magnesium delayed-release tablets tightly closed to protect from moisture.

Keep naproxen and esomeprazole magnesium delayed-release tablets and all medicines out of the reach of children.

What are the ingredients in naproxen and esomeprazole magnesium delayed-release tablets?
Active ingredients: naproxen and esomeprazole magnesium
Inactive ingredients: microcrystalline cellulose, croscarmellose sodium, povidone, colloidal silicon dioxide, magnesium stearate, methacrylic acid and ethyl acrylate copolymer, talc, triethy citrate, hypromellose, macrogol, sodium lauryl sulfate, magnesium oxide, polyethylene glycol, ferric oxide yellow. The imprinting ink contains shellac glaze, black iron oxide, propylene glycol, ammonium hydroxide.

General information about the safe and effective use of naproxen and esomeprazole magnesium delayed-release tablets.
Medicines are sometimes prescribed for purposes other than those listed in a Medication Guide. Do not use naproxen and esomeprazole magnesium delayed-release tablets for a condition for which it was not prescribed. Do not give naproxen and esomeprazole magnesium delayed-release tablets to other people, even if they have the same symptoms that you have. It may harm them. You can ask your healthcare provider or pharmacist for information about naproxen and esomeprazole magnesium delayed-release tablets that is written for health professionals.
Product of India
Manufactured by:
Ajanta Pharma Limited, India
Marketed by:
Ajanta Pharma USA Inc.
Bridgewater, NJ 08807.
#All trademarks are the properties of their respective owners
This Medication Guide has been approved by the U.S. Food and Drug Administration.
Revised: 08/2025

Repackaged By: Preferred Pharmaceuticals Inc.

PACKAGE LABEL.PRINCIPAL DISPLAY PANEL

NDC 68788-8766
Repackaged By: Preferred Pharmaceuticals Inc.

Naproxen and Esomeprazole Magnesium Delayed-Release Tablets
500 mg/20 mg*
PHARMACIST: Dispense the enclosed Medication Guide to each patient.
Rx Only
ajanta